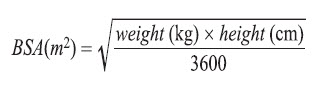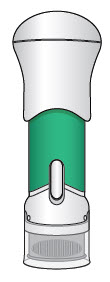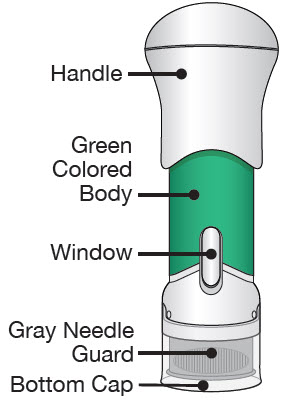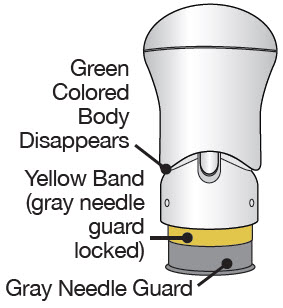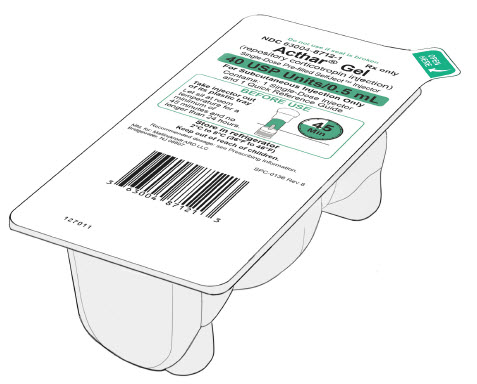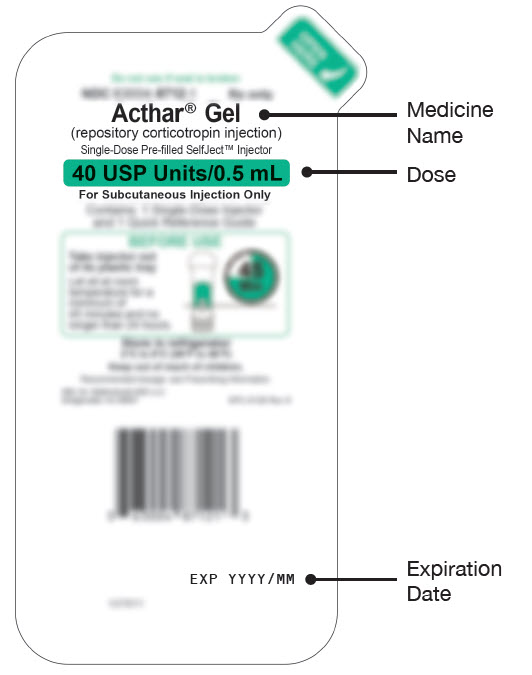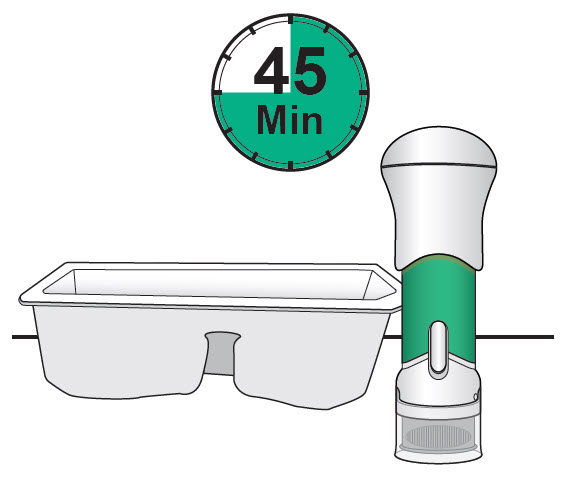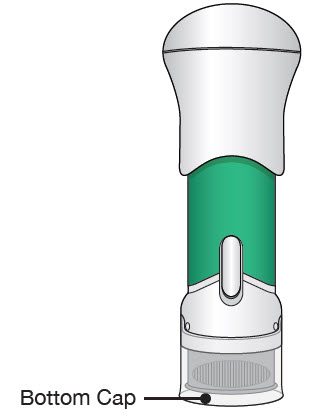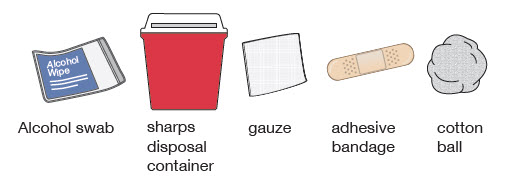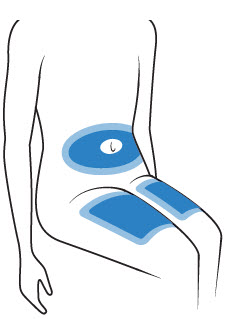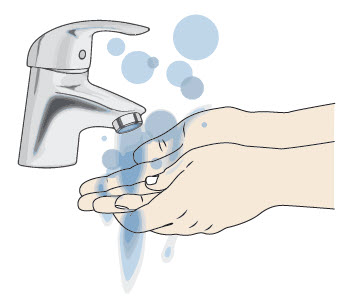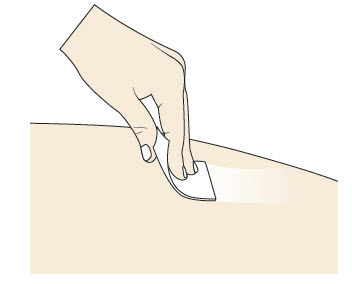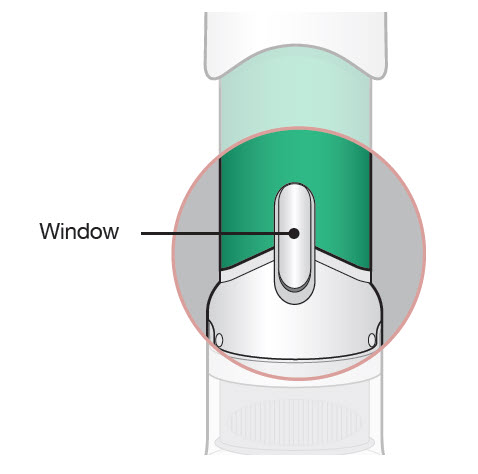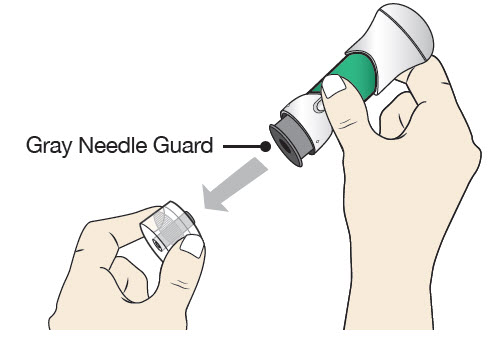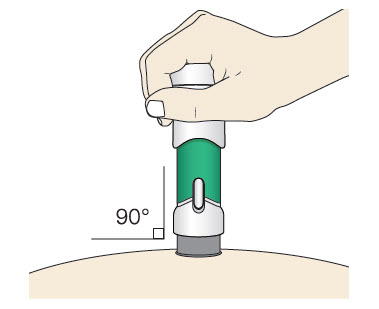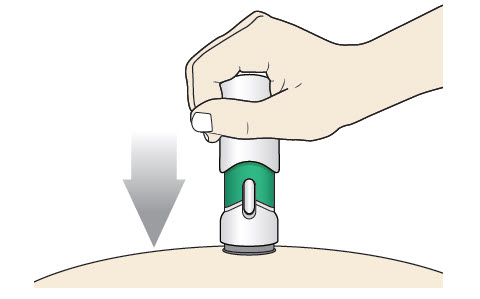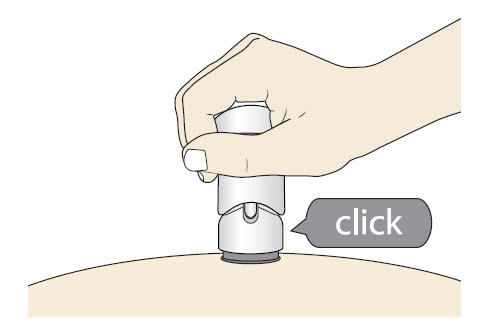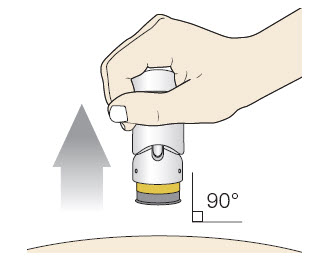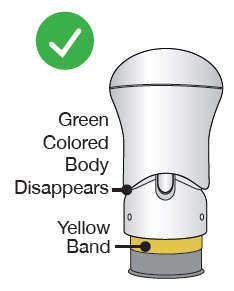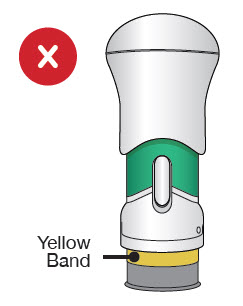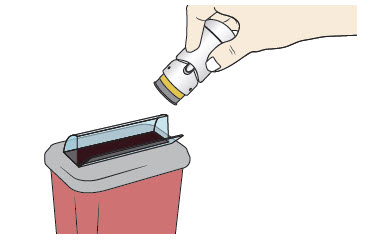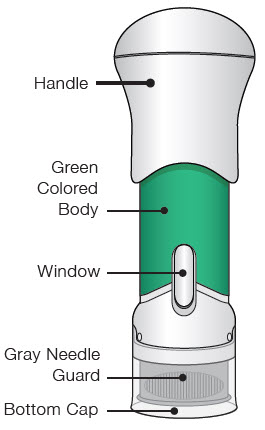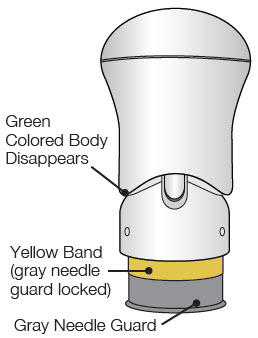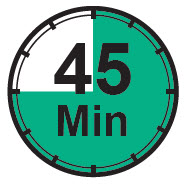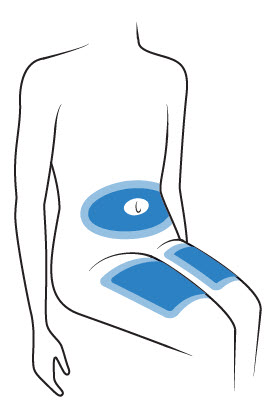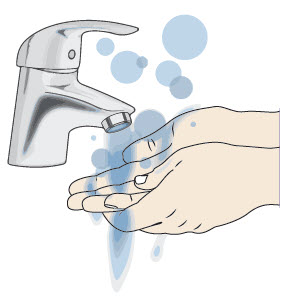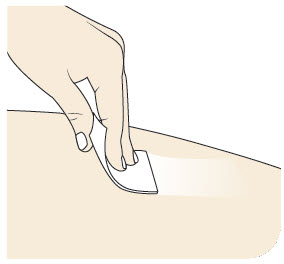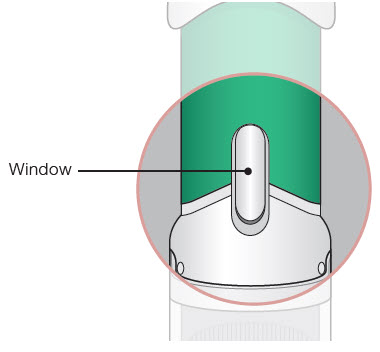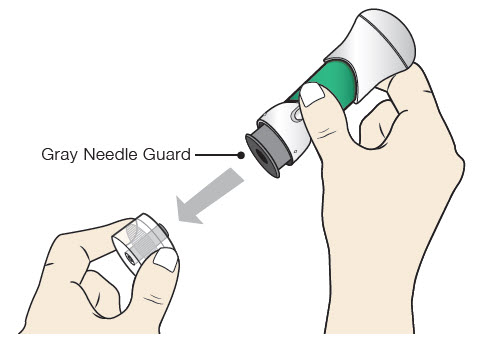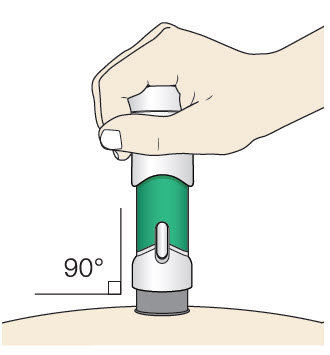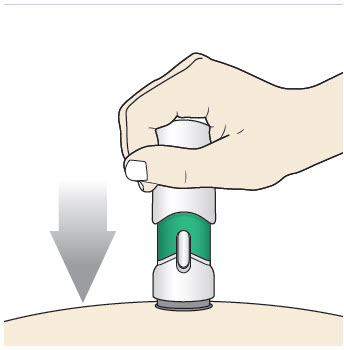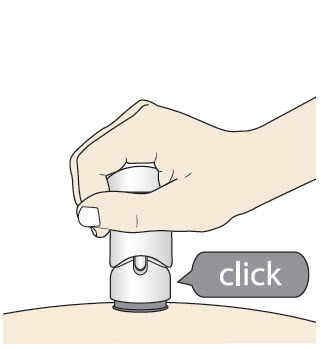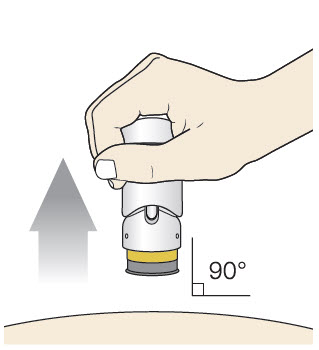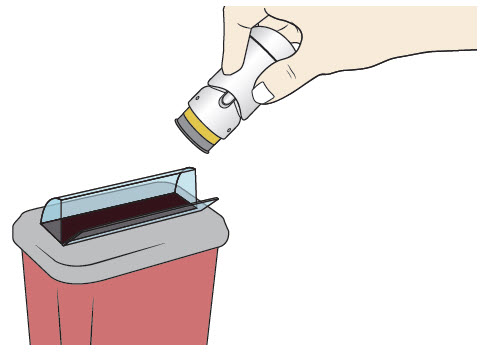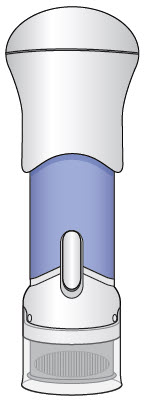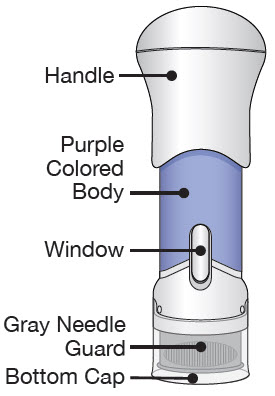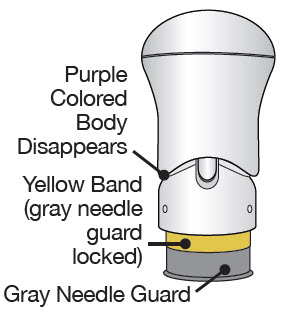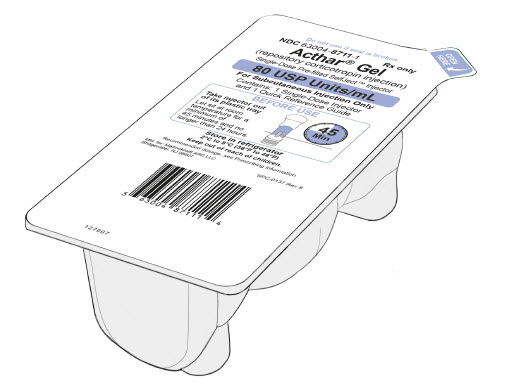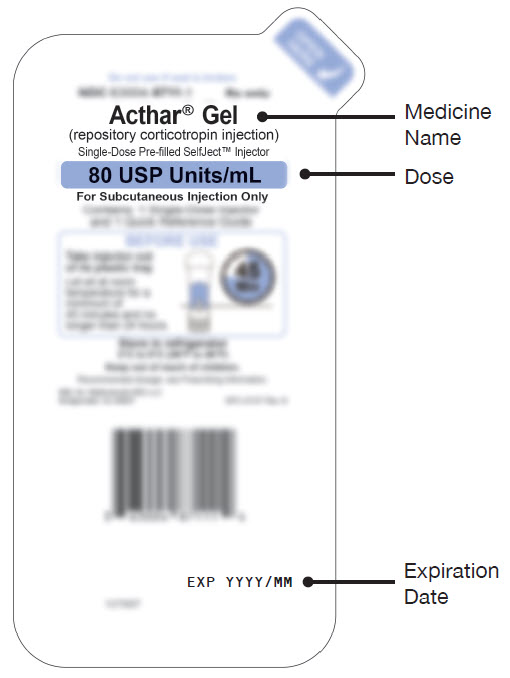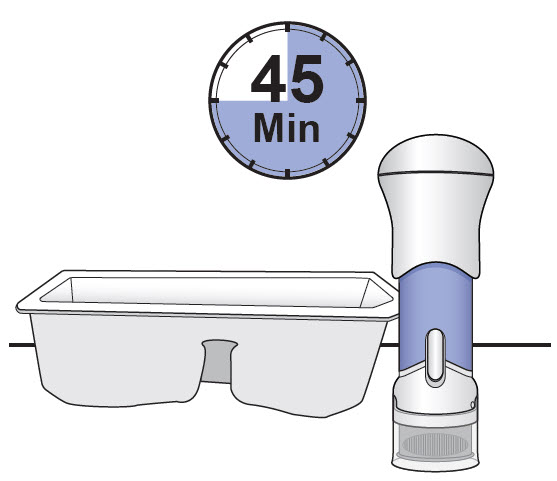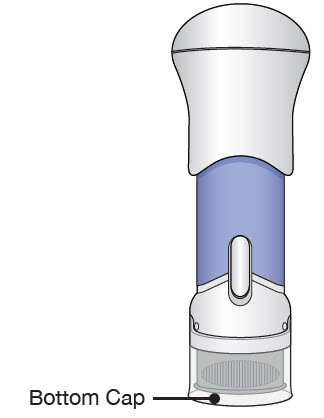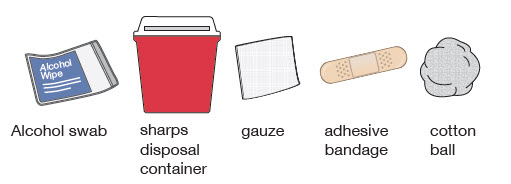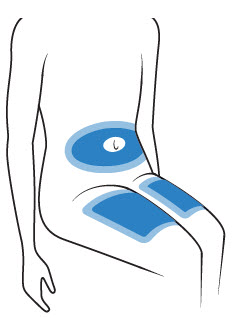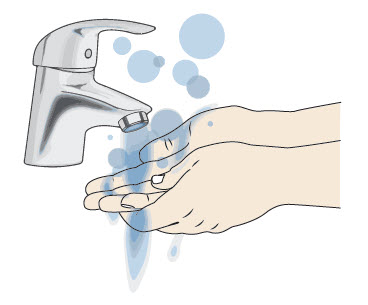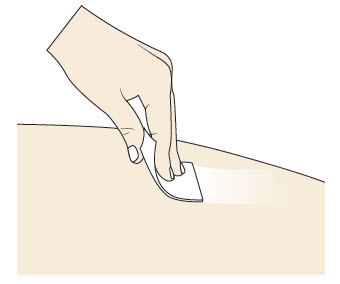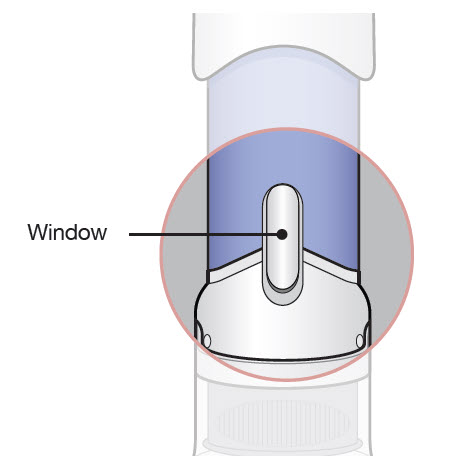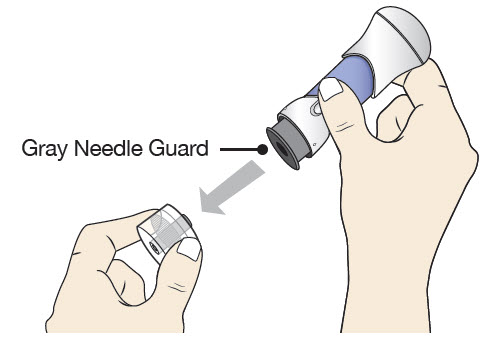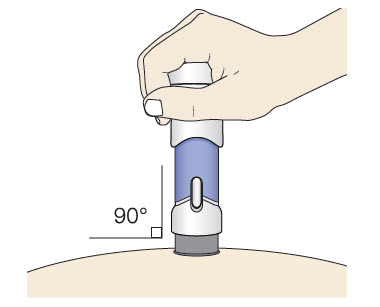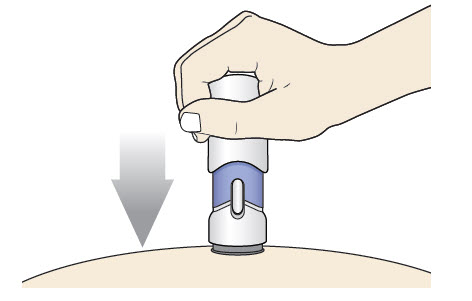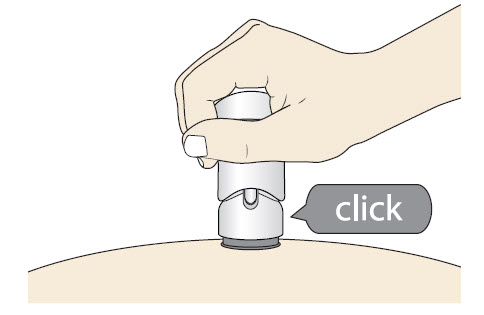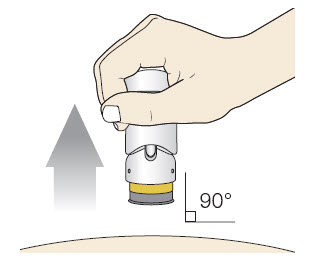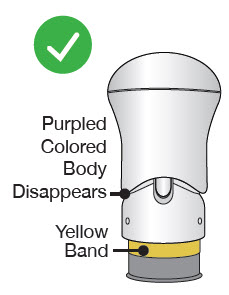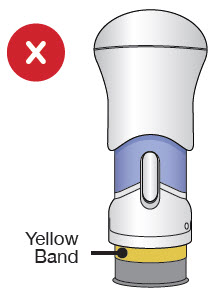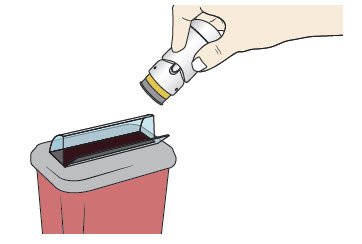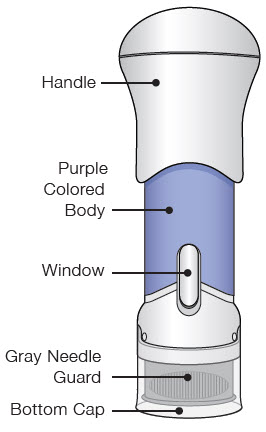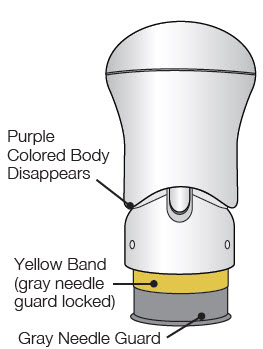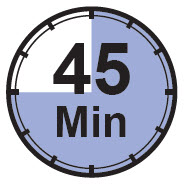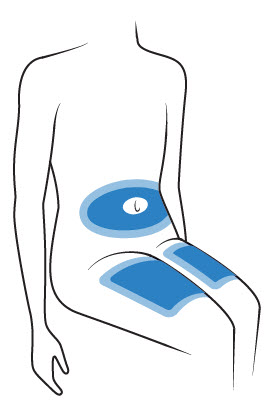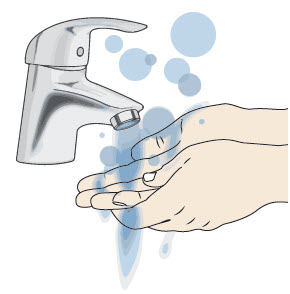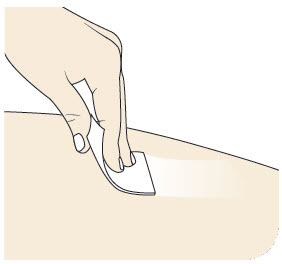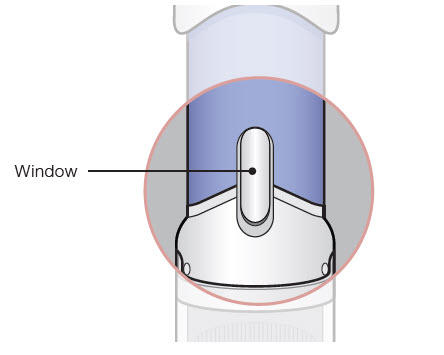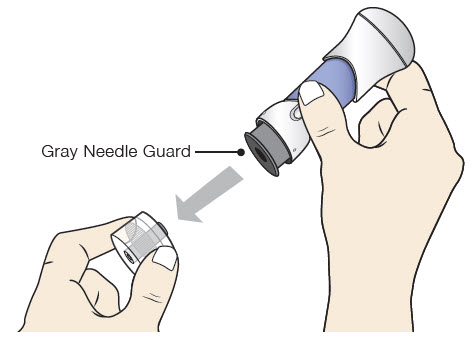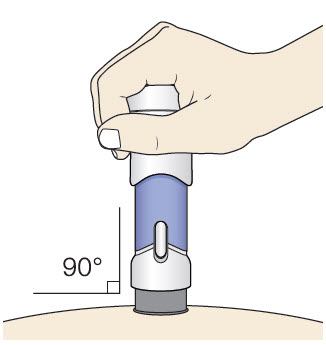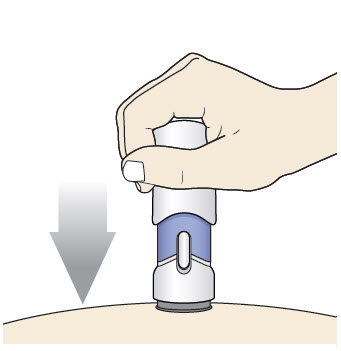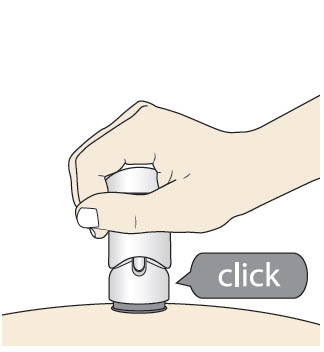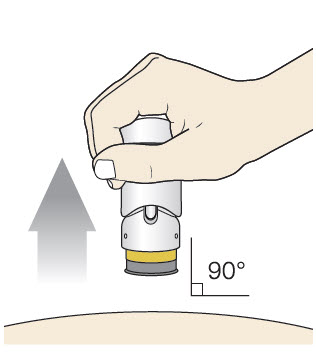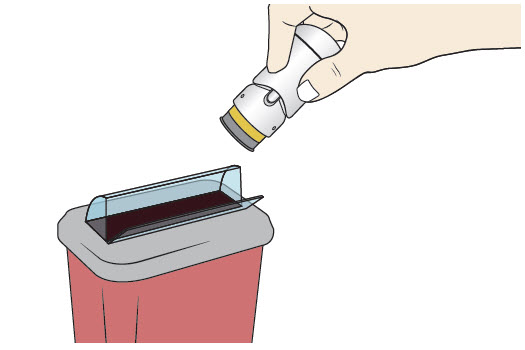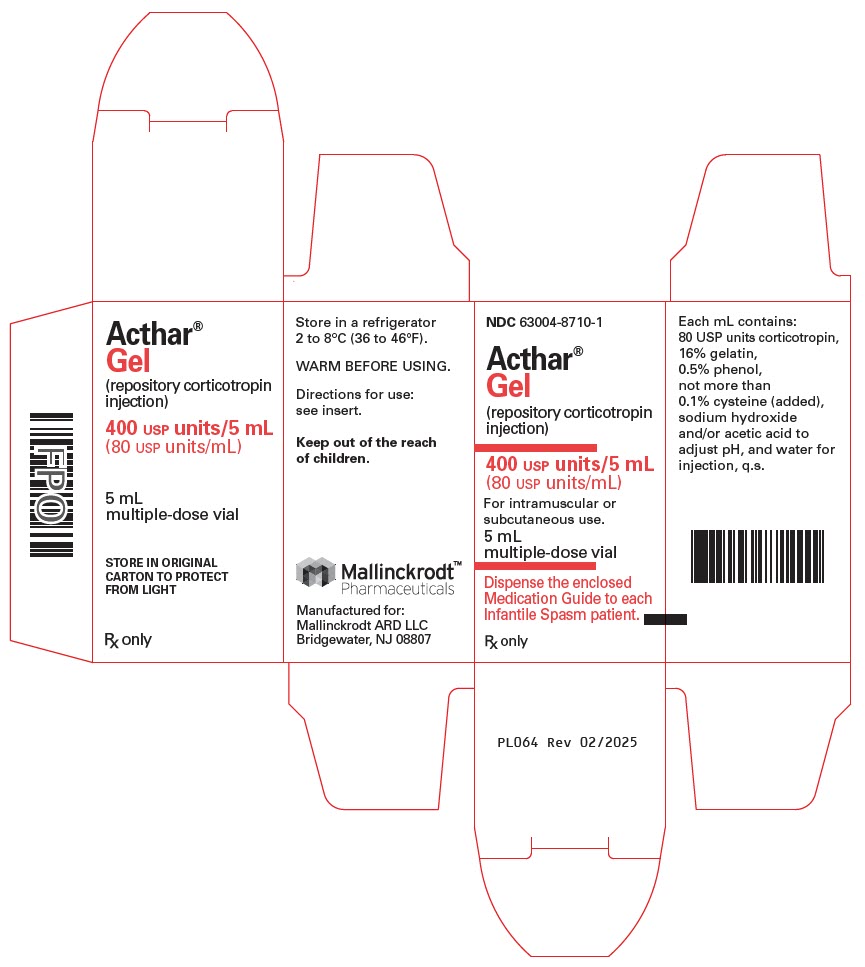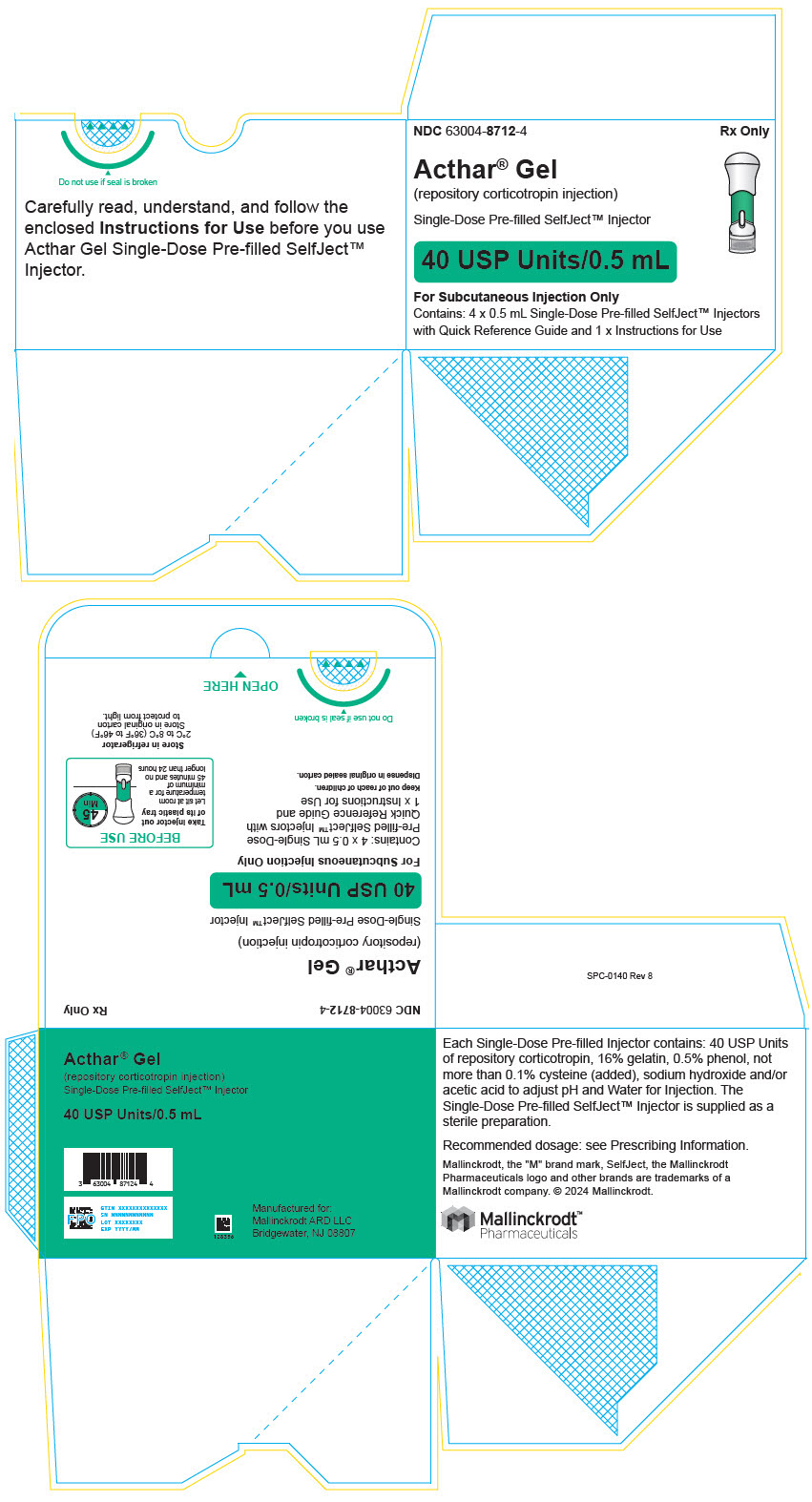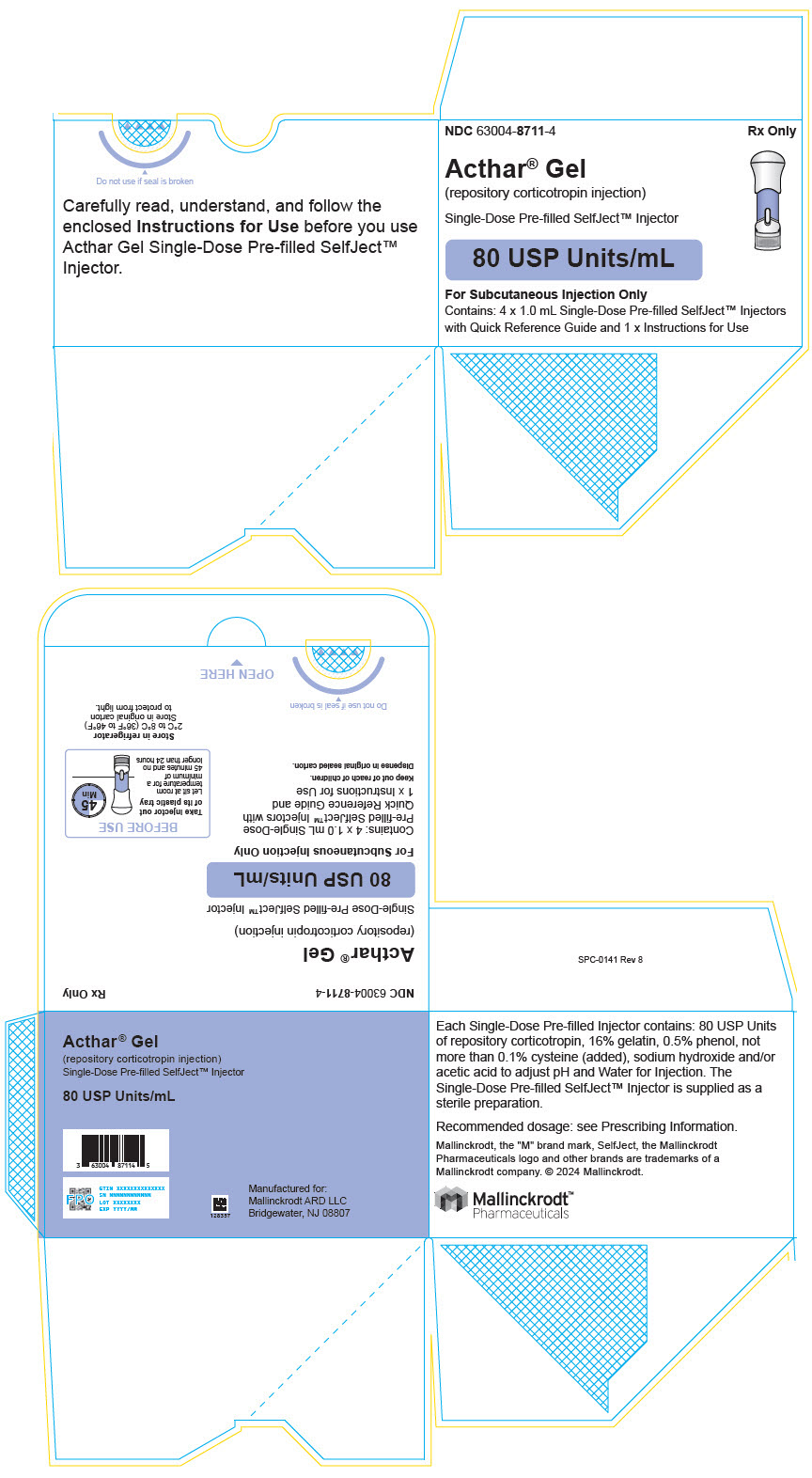 DRUG LABEL: Acthar
NDC: 63004-8710 | Form: INJECTION
Manufacturer: Mallinckrodt ARD LLC
Category: prescription | Type: HUMAN PRESCRIPTION DRUG LABEL
Date: 20251205

ACTIVE INGREDIENTS: CORTICOTROPIN 80 [USP'U]/1 mL
INACTIVE INGREDIENTS: GELATIN, UNSPECIFIED; PHENOL; CYSTEINE; SODIUM HYDROXIDE; ACETIC ACID; WATER

HIGHLIGHTS OF PRESCRIBING INFORMATION

These highlights do not include all the information needed to use ACTHAR® GEL safely and effectively. See full prescribing information for ACTHAR GEL.
ACTHAR GEL (repository corticotropin injection), for intramuscular or subcutaneous use
Initial U.S. Approval: 1952

RECENT MAJOR CHANGES

Dosage and Administration (2.1, 2.5) | 02/2024

1 INDICATIONS AND USAGE

- Acthar Gel is indicated as monotherapy for the treatment of infantile spasms in infants and children under 2 years of age. (1.1)
- Acthar Gel is indicated for the treatment of exacerbations of multiple sclerosis in adults. (1.2)
- Acthar Gel may be used for the following disorders and diseases: rheumatic (1.3); collagen (1.4); dermatologic (1.5); allergic states (1.6); ophthalmic (1.7); respiratory (1.8); and edematous state. (1.9)

2 DOSAGE AND ADMINISTRATION

- Acthar Gel vial is for either intramuscular or subcutaneous injection. (2.1)
- Acthar Gel single-dose pre-filled SelfJect injector:
  - is for subcutaneous administration by adults only. (2.1)
  - used to administer single doses of 40 units or 80 units only. (2.1)
- Infantile spasms: doses must be administered intramuscularly using the Acthar gel vial. The recommended dose is 150 U/m^2 divided into twice daily injections of 75 U/m^2. After 2 weeks of treatment dosing should be gradually tapered and discontinued over a 2-week period. Acthar Gel single-dose pre-filled SelfJect injector is not to be used for the treatment of infantile spasms (2.2)
- Acute exacerbations of multiple sclerosis: daily intramuscular or subcutaneous doses of 80 to 120 units for 2-3 weeks may be administered. It may be necessary to taper the dose. (2.3)
- Other disorders and diseases: individualize dosing depending on the disease and patient. The usual dose is 40 to 80 units given intramuscularly or subcutaneously every 24 to 72 hours. It may be necessary to taper the dose. (2.4)

3 DOSAGE FORMS AND STRENGTHS

Injection available as:

- 5 mL multi-dose vial containing 80 USP units/mL, for intramuscular or subcutaneous use. (3)
- 40 USP Units/0.5 mL Acthar Gel single-dose pre-filled SelfJect injector for subcutaneous injection. (3)
- 80 USP Units/mL Acthar Gel single-dose pre-filled SelfJect injector for subcutaneous injection. (3)

4 CONTRAINDICATIONS

Acthar Gel is contraindicated:

- for intravenous administration (4)
- in infants under 2 years of age who have suspected congenital infections (4)
- with concomitant administration of live or live attenuated vaccines in patients receiving immunosuppressive doses of Acthar Gel (4)
- in patients with scleroderma, osteoporosis, systemic fungal infections, ocular herpes simplex, recent surgery, history of or the presence of a peptic ulcer, congestive heart failure, uncontrolled hypertension, primary adrenocortical insufficiency, adrenocortical hyperfunction, or sensitivity to proteins of porcine origin (4)

5 WARNINGS AND PRECAUTIONS

- Infections: Increased susceptibility to new infection and increased risk of exacerbation, dissemination or reactivation of latent infections. Signs and symptoms of infection may be masked. (5.1)
- Adrenal Insufficiency after Prolonged Therapy: Monitor for effects of hypothalamic-pituitary-adrenal axis suppression after stopping treatment. (5.2)
- Cushing's Syndrome: May occur after prolonged therapy. Monitor for signs and symptoms. (5.2)
- Elevated Blood Pressure, Salt and Water Retention, and Hypokalemia: Monitor blood pressure and sodium and potassium levels. (5.3)
- Masking of Symptoms of Other Underlying Disease/Disorders: Monitor patients for signs of other underlying disease/disorders that may be masked. (5.5)
- Gastrointestinal Perforation and Bleeding: There is a risk for gastric ulcers and bleeding. There is an increased risk of perforation in patients with certain GI disorders. Signs and symptoms may be masked. Monitor for signs of perforation and bleeding. (5.6)
- Behavioral and Mood Disturbances: May include euphoria, insomnia, mood swings, personality changes, severe depression and psychosis. Existing conditions may be aggravated. (5.7)
- Comorbid Diseases: Symptoms of diabetes and myasthenia gravis may be worsened with treatment. (5.8)
- Ophthalmic Effects: Monitor for cataracts, infections and glaucoma. (5.9)
- Immunogenicity Potential: Neutralizing antibodies with chronic administration may lead to a loss of endogenous ACTH activity. (5.10)
- Use in Patients with Hypothyroidism or Liver Cirrhosis: May result in an enhanced effect. (5.11)
- Negative Effects on Growth and Physical Development: Monitor pediatric patients on long term therapy. (5.12)
- Decrease in Bone Density: Monitor for osteoporosis in patients on long term therapy. (5.13)

6 ADVERSE REACTIONS

- Commonly reported postmarketing adverse reactions for Acthar Gel include injection site reaction, asthenic conditions (including fatigue, malaise, asthenia and lethargy), fluid retention (including peripheral swelling), insomnia, headache, and blood glucose increased. (6.2)
- The most common adverse reactions (5% or greater in the recommended twice daily dosing group) for the treatment of infantile spasms are increased risk of infections, convulsions, hypertension, irritability, and pyrexia. (6.1)

To report SUSPECTED ADVERSE REACTIONS, contact Mallinckrodt at 1-800-844-2830 or FDA at 1-800-FDA-1088 or www.fda.gov/medwatch.

7 DRUG INTERACTIONS

- Acthar Gel may accentuate electrolyte loss associated with diuretics. (7)

8 USE IN SPECIFIC POPULATIONS

- Pediatric Use: Prolonged use of Acthar Gel in children may inhibit skeletal growth. If use is necessary, it should be given intermittently with careful observation. (5.12, 5.13, and 8.4)
- Pregnancy: May cause fetal harm. (8.1)

FULL PRESCRIBING INFORMATION

1 INDICATIONS AND USAGE

1.1 Infantile Spasms

Acthar Gel is indicated as monotherapy for the treatment of infantile spasms in infants and children under 2 years of age.

1.2 Multiple Sclerosis

Acthar Gel is indicated for the treatment of acute exacerbations of multiple sclerosis in adults. Controlled clinical trials have shown Acthar Gel to be effective in speeding the resolution of acute exacerbations of multiple sclerosis. However, there is no evidence that it affects the ultimate outcome or natural history of the disease.

1.3 Rheumatic Disorders

As adjunctive therapy for short-term administration (to tide the patient over an acute episode or exacerbation) in: Psoriatic arthritis; Rheumatoid arthritis, including juvenile rheumatoid arthritis (selected cases may require low-dose maintenance therapy); Ankylosing spondylitis.

1.4 Collagen Diseases

During an exacerbation or as maintenance therapy in selected cases of: systemic lupus erythematosus, systemic dermatomyositis (polymyositis).

1.5 Dermatologic Diseases

Severe erythema multiforme, Stevens-Johnson syndrome.

1.6 Allergic States

Serum sickness.

1.7 Ophthalmic Diseases

Severe acute and chronic allergic and inflammatory processes involving the eye and its adnexa such as: keratitis; iritis, iridocyclitis, diffuse posterior uveitis and choroiditis, optic neuritis, chorioretinitis; anterior segment inflammation.

1.8 Respiratory Diseases

Symptomatic sarcoidosis.

1.9 Edematous State

To induce a diuresis or a remission of proteinuria in the nephrotic syndrome without uremia of the idiopathic type or that due to lupus erythematosus.

2 DOSAGE AND ADMINISTRATION

2.1 Important Information

Acthar Gel vial is intended for either intramuscular or subcutaneous injection.

Acthar Gel single-dose pre-filled SelfJect injector is for subcutaneous administration by adults (18 years of age and older) only. The single-dose pre-filled SelfJect injector should only be used to administer single doses of either 40 units or 80 units. For administration of doses other than 40 units or 80 units, use the Acthar Gel multi-dose vial.

2.2 Recommended Dosage for Infantile Spasms in Infants and Children Under 2 Years of Age

In the treatment of infantile spasms, Acthar Gel must be administered intramuscularly using the Acthar gel vial. Do not use the Acthar Gel single-dose pre-filled SelfJect injector for the treatment of infantile spasms. The recommended regimen is a daily dose of 150 U/m^2 (divided into twice daily intramuscular (IM) injections of 75 U/m^2) administered over a 2-week period. Dosing with Acthar Gel should then be gradually tapered over a 2-week period to avoid adrenal insufficiency. The following is one suggested tapering schedule: 30 U/m^2 in the morning for 3 days; 15 U/m^2 in the morning for 3 days; 10 U/m^2 in the morning for 3 days; and 10 U/m^2 every other morning for 6 days.

Acthar Gel is typically dosed based on body surface area (BSA). For calculation of body surface area, use the following formula:

2.3 Recommended Dosage for the Treatment of Acute Exacerbations in Adults with Multiple Sclerosis

The recommended dose is daily intramuscular or subcutaneous doses of 80 to 120 units for 2-3 weeks for acute exacerbations.

Dosage should be individualized according to the medical condition of each patient. Frequency and dose of the drug should be determined by considering the severity of the disease and the initial response of the patient.

Although drug dependence does not occur, sudden withdrawal of Acthar Gel after prolonged use may lead to adrenal insufficiency or recurrent symptoms which make it difficult to stop the treatment. It may be necessary to taper the dose and increase the injection interval to gradually discontinue the medication.

2.4 Recommended Dosage for Other Indications for Adults and Children Over 2 Years of Age

Dosage should be individualized according to the disease under treatment and the general medical condition of each patient. Frequency and dose of the drug should be determined by considering severity of the disease and the initial response of the patient.

The usual dose of Acthar Gel is 40 to 80 units given intramuscularly or subcutaneously every 24 to 72 hours.

Although drug dependence does not occur, sudden withdrawal of Acthar Gel after prolonged use may lead to adrenal insufficiency or recurrent symptoms which make it difficult to stop the treatment. It may be necessary to taper the dose and increase the injection interval to gradually discontinue the medication.

2.5 Preparation and Administration

Visually inspect the liquid for particulate matter and discoloration prior to administration. Acthar Gel must not be injected if the solution is cloudy or contains particulate matter.

Acthar Gel Multi-Dose Vial

- Warm to room temperature before using.
- Take caution to not over-pressurize the vial prior to withdrawing the product.

Acthar Gel Single-Dose Pre-filled SelfJect Injector

Preparation

- Prior to injection, remove from the refrigerator and sealed tray and allow to sit for 45 minutes to warm to room temperature.

Administration

- Read the FDA-approved Instructions for Use carefully before administering.
- Administer by subcutaneous injection only. Acthar Gel single-dose pre-filled SelfJect injector is not for intramuscular injection.
- Inject in the upper thigh, abdomen, or back of arm. Avoid injecting within 1 inch of navel, knee, or groin area.
- Avoid areas with scars, tattoos, warts, birthmarks, or stretch marks, or where the skin is irritated.
- Rotate injection sites. Do not use the same site more than one time per week.

3 DOSAGE FORMS AND STRENGTHS

Injection available as:

400 USP Units/5 mL (80 USP Units/mL) in a multi-dose vial for subcutaneous or intramuscular injection.

40 USP Units/0.5 mL in a single-dose pre-filled SelfJect injector for subcutaneous injection.

80 USP Units/mL in a single-dose pre-filled SelfJect injector for subcutaneous injection.

Acthar Gel (repository corticotropin injection) is a clear light amber solution mobile at room temperature.

4 CONTRAINDICATIONS

Acthar Gel is contraindicated:

- for intravenous administration.
- in infants under 2 years of age who have suspected congenital infections.
- with concomitant administration of live or live attenuated vaccines in patients receiving immunosuppressive doses of Acthar Gel.
- in patients with scleroderma, osteoporosis, systemic fungal infections, ocular herpes simplex, recent surgery, history of or the presence of a peptic ulcer, congestive heart failure, uncontrolled hypertension, primary adrenocortical insufficiency, adrenocortical hyperfunction, or sensitivity to proteins of porcine origin.

5 WARNINGS AND PRECAUTIONS

The adverse effects of Acthar Gel are related primarily to its steroidogenic effects. Not all of the adverse events described below have been seen after treatment with Acthar Gel, but they might be expected to occur because they are steroidogenic effects [see Adverse Reactions (6.3)].

5.1 Infections

Acthar Gel may increase the risks related to infections with any pathogen, including viral, bacterial, fungal, protozoan or helminthic infections. Patients with latent tuberculosis or tuberculin reactivity should be observed closely, and if therapy is prolonged, chemoprophylaxis should be instituted.

5.2 Cushing's Syndrome and Adrenal Insufficiency Upon Withdrawal

Treatment with Acthar Gel can cause hypothalamic-pituitary-adrenal (HPA) axis suppression and Cushing's syndrome. These conditions should be monitored especially with chronic use.

Suppression of the HPA may occur following prolonged therapy with the potential for adrenal insufficiency after withdrawal of the medication. Patients should be monitored for signs of insufficiency such as weakness, hyperpigmentation, weight loss, hypotension and abdominal pain.

The symptoms of adrenal insufficiency in infants treated for infantile spasms can be difficult to identify. The symptoms are non-specific and may include anorexia, fatigue, lethargy, weakness, excessive weight loss, hypotension and abdominal pain. It is critical that parents and caregivers be made aware of the possibility of adrenal insufficiency when discontinuing Acthar Gel and should be instructed to observe for, and be able to recognize, these symptoms [see Patient Counseling Information (17)].

The recovery of the adrenal gland may take from days to months so patients should be protected from the stress (e.g., trauma or surgery) by the use of corticosteroids during the period of stress.

The adrenal insufficiency may be minimized by tapering of the dose when discontinuing treatment.

Signs or symptoms of Cushing's syndrome may occur during therapy but generally resolve after therapy is stopped. Patients should be monitored for these signs and symptoms such as deposition of adipose tissue in characteristics sites (e.g., moon face, truncal obesity), cutaneous striae, easy bruisability, decreased bone mineralization, weight gain, muscle weakness, hyperglycemia, and hypertension.

5.3 Elevated Blood Pressure, Salt and Water Retention, and Hypokalemia

Acthar Gel can cause elevation of blood pressure, salt and water retention, and increased excretion of potassium and calcium. Dietary salt restriction and potassium supplementation may be necessary. Caution should be used in the treatment of patients with hypertension or renal insufficiency. Acthar Gel is contraindicated in patients with congestive heart failure [see Contraindications (4)].

5.4 Vaccination

Administration of live or live attenuated vaccines is contraindicated in patients receiving immunosuppressive doses of Acthar Gel. Killed or inactivated vaccines may be administered; however, the response to such vaccines can not be predicted. Other immunization procedures should be undertaken with caution in patients who are receiving Acthar Gel, especially when high doses are administered, because of the possible hazards of neurological complications and lack of antibody response.

5.5 Masking Symptoms of Other Diseases

Acthar Gel often acts by masking symptoms of other diseases/disorders without altering the course of the other disease/disorder. Patients should be monitored carefully during and for a period following discontinuation of therapy for signs of infection, abnormal cardiac function, hypertension, hyperglycemia, change in body weight and fecal blood loss.

5.6 Gastrointestinal Perforation and Bleeding

Acthar Gel can cause GI bleeding and gastric ulcer. There is also an increased risk for perforation in patients with certain gastrointestinal disorders. Signs of gastrointestinal perforation, such as peritoneal irritation, may be masked by the therapy. Use caution where there is the possibility of impending perforation, abscess or other pyogenic infections, diverticulitis, fresh intestinal anastomoses, and active or latent peptic ulcer.

5.7 Behavioral and Mood Disturbances

Use of Acthar Gel may be associated with central nervous system effects ranging from euphoria, insomnia, irritability (especially in infants), mood swings, personality changes, and severe depression, to frank psychotic manifestations. Also, existing emotional instability or psychotic tendencies may be aggravated. These effects are reversible once Acthar Gel therapy is stopped.

5.8 Comorbid Diseases

Patients with a comorbid disease may have that disease worsened. Caution should be used when prescribing Acthar Gel in patients with diabetes and myasthenia gravis.

5.9 Ophthalmic Effects

Prolonged use of Acthar Gel may produce posterior subcapsular cataracts, glaucoma with possible damage to the optic nerves and may enhance the establishment of secondary ocular infections due to fungi and viruses.

5.10 Immunogenicity Potential

Acthar Gel is immunogenic. Limited available data suggest that a patient may develop antibodies to Acthar Gel after chronic administration and loss of endogenous ACTH and Acthar Gel activity. Prolonged administration of Acthar Gel may increase the risk of hypersensitivity reactions. Cases of anaphylaxis have been reported in the postmarketing setting. Use in patients with sensitivity to porcine protein is contraindicated, and the possibility of sensitivity should be considered during the course of treatment should symptoms arise.

5.11 Use in Patients with Hypothyroidism or Liver Cirrhosis

There is an enhanced effect in patients with hypothyroidism and in those with cirrhosis of the liver.

5.12 Negative Effects on Growth and Physical Development

Long-term use of Acthar Gel may have negative effects on growth and physical development in pediatric patients. Changes in appetite are seen with Acthar Gel therapy, with the effects becoming more frequent as the dose or treatment period increases. These effects are reversible once Acthar Gel therapy is stopped. Growth and physical development of pediatric patients on prolonged therapy should be carefully monitored.

5.13 Decrease in Bone Density

Decrease in bone formation and an increase in bone resorption both through an effect on calcium regulation (i.e., decreasing absorption and increasing excretion) and inhibition of osteoblast function may occur. These, together with a decrease in the protein matrix of the bone (secondary to an increase in protein catabolism) and reduced sex hormone production, may lead to inhibition of bone growth in children and adolescents and to the development of osteoporosis at any age. Special consideration should be given to patients at increased risk of osteoporosis (i.e., postmenopausal women) before initiating therapy, and bone density should be monitored in patients on long term therapy.

6 ADVERSE REACTIONS

The following clinically significant adverse reactions are described elsewhere in the labeling:

- Infections [see Warnings and Precautions (5.1)]
- Cushing's Syndrome and Adrenal Insufficiency Upon Withdrawal [see Warnings and Precautions (5.2)]
- Elevated Blood Pressure, Salt and Water Retention, and Hypokalemia [see Warnings and Precautions (5.3)]
- Masking Symptoms of Other Diseases [see Warnings and Precautions (5.5)]
- Gastrointestinal Perforation and Bleeding [see Warnings and Precautions (5.6)]
- Behavioral and Mood Disturbances [see Warnings and Precautions (5.7)]
- Ophthalmic Effects [see Warnings and Precautions (5.9)]
- Immunogenicity Potential [see Warnings and Precautions (5.10)]
- Negative Effects on Growth and Physical Development [see Warnings and Precautions (5.12)]
- Decrease in Bone Density [see Warnings and Precautions (5.13)]

6.1 Clinical Trials Experience

Because clinical trials are conducted under widely varying conditions, adverse reaction rates observed in the clinical trials of a drug cannot be directly compared to rates in the clinical trials of another drug and may not reflect the rates observed in practice.

Adverse Reactions in Infants and Children Under 2 Years of Age

While the types of adverse reactions seen in infants and children under age 2 treated for infantile spasms are similar to those seen in older patients, their frequency and severity may be different due to the very young age of the infant, the underlying disorder, the duration of therapy and the dosage regimen. Below is a summary of adverse reactions specifically tabulated from source data derived from retrospective chart reviews and clinical trials in children under 2 years of age treated for infantile spasms. The number of patients in controlled trials at the recommended dose was too few to provide meaningful incidence rates or to permit a meaningful comparison to the control groups. The most common adverse reactions (5% or greater in the recommended twice daily dosing group) for the treatment of infantile spasms are increased risk of infections, convulsions, hypertension, irritability, and pyrexia.

TABLE: Incidence (%) of Adverse Reactions Occurring in ≥2% of Infants and Children Under 2 Years of Age Treated with Acthar Gel
Adverse Reactions | Recommended 75 U/m^2 twice daily n=122, (%) | 150 U/m^2 once daily n=37 (%)
Cardiac disorders
Cardiac Hypertrophy | 3 | 0
Endocrine disorders
Cushingoid | 3 | 22
Gastrointestinal disorders
Diarrhea | 3 | 14
Vomiting | 3 | 5
Constipation | 0 | 5
General disorders and administration site conditions
Irritability | 7 | 19
Pyrexia | 5 | 8
Infections and infestations
Infection [Specific infections that occurred at ≥2% were candidiasis, otitis media, pneumonia and upper respiratory tract infections.] | 20 | 46
Investigations
Weight gain | 1 | 3
Metabolism and nutrition disorders
Increased appetite | 0 | 5
Decreased appetite | 3 | 3
Nervous system disorders
Convulsion [In the treatment of infantile spasms, other types of seizures/convulsions may occur because some patients with infantile spasms progress to other forms of seizures (for example, Lennox-Gastaut Syndrome). Additionally, the spasms sometimes mask other seizures and once the spasms resolve after treatment, the other seizures may become visible.] | 12 | 3
Respiratory, thoracic and mediastinal disorders
Nasal Congestion | 1 | 5
Skin and subcutaneous tissue disorders
Acne | 0 | 14
Rash | 0 | 8
Vascular disorders
Hypertension | 11 | 19

These adverse reactions may also be seen in adults and children over 2 years of age when treated for other purposes and with different doses and regimens.

6.2 Postmarketing Experience

The following adverse reactions have been identified during post approval use of Acthar Gel.

Because adverse reactions are reported voluntarily from a population of uncertain size, it is not always possible to reliably estimate their frequency or establish a causal relationship to drug exposure.

Allergic Reactions

Allergic responses have presented as dizziness, nausea, and anaphylaxis (anaphylactic shock, hypotension, respiratory compromise, urticaria, edema).

Cardiovascular

Necrotizing angitis (adults only), congestive heart failure, atrial fibrillation, and palpitations.

Dermatologic

Skin thinning (adults only), facial erythema, and increased sweating (adults only).

Endocrine

Decreased carbohydrate tolerance (infants only), hirsutism, and menstrual irregularities.

Gastrointestinal

Pancreatitis (adults only), abdominal distention, and ulcerative esophagitis.

General Disorders and Administration Site Conditions

Injection site reaction and asthenic conditions (including fatigue, malaise, asthenia, and lethargy).

Infections and Infestations

Abscess.

Investigations

Blood glucose increased.

Metabolic

Hypokalemic alkalosis (infants only) and fluid retention (including peripheral swelling).

Musculoskeletal

Muscle weakness and vertebral compression fractures (infants only).

Neurological

Headache (adults only), vertigo (adults only), subdural hematoma, intracranial hemorrhage (adults only), and reversible brain shrinkage (usually secondary to hypertension) (infants only).

Psychiatric Disorders

Insomnia.

6.3 Possible Additional Steroidogenic Effects

Based on steroidogenic effects of Acthar Gel certain adverse events may be expected due to the pharmacological effects of corticosteroids. The adverse events that may occur but have not been reported for Acthar Gel are:

Dermatologic

Impaired wound healing, petechiae and ecchymoses, and suppression of skin test reactions.

Metabolic

Negative nitrogen balance due to protein catabolism and alteration in glucose tolerance.

Musculoskeletal

Loss of muscle mass and aseptic necrosis of femoral and humeral heads.

Neurological

Increased intracranial pressure with papilledema, (pseudo-tumor cerebri) usually after treatment, and subdural effusion.

Ophthalmic

Exophthalmos.

7 DRUG INTERACTIONS

Formal drug-drug interaction studies have not been performed.

Acthar Gel may accentuate the electrolyte loss associated with diuretic therapy.

8 USE IN SPECIFIC POPULATIONS

8.1 Pregnancy

Risk Summary

Based on Acthar Gel's pharmacological effect of stimulating an endogenous steroid response [see Clinical Pharmacology (12.1)], Acthar Gel may cause fetal harm when administered to a pregnant woman. The published literature on systemic corticosteroid use during pregnancy, which may be relevant, suggests potential concerns. Intrauterine growth restriction, decreased birth weight, and preterm birth have been reported with maternal use of corticosteroids; however, the underlying maternal condition may also contribute to these risks. Hypoadrenalism has also been reported in infants after high-dose and/or long-term use of corticosteroids during pregnancy (see Clinical Considerations). The potential adverse developmental effects of Acthar Gel have not been adequately assessed in animals.

The estimated background risk of major birth defects and miscarriage for the indicated population(s) is unknown. All pregnancies have a background risk of birth defects, loss, or other adverse outcomes. In the U.S. general population, the estimated background risk of major birth defects and miscarriage in clinically recognized pregnancies is 2% to 4% and 15% to 20%, respectively.

Clinical Considerations

Fetal-Neonatal Adverse Reactions

Hypoadrenalism has been reported in infants born to mothers treated with systemic corticosteroids during pregnancy. Infants born to mothers treated with Acthar Gel should be carefully observed for signs of hypoadrenalism, such as poor feeding, irritability, weakness, and vomiting, and managed accordingly [see Warnings and Precautions (5.2)].

8.2 Lactation

Risk Summary

There are no available data on the presence of corticotropin in either human or animal milk, the effects on the breastfed infant, or on milk production. The developmental and health benefits of breastfeeding should be considered along with the mother's clinical need for Acthar Gel and any potential adverse effects on the breastfed infant from Acthar Gel or from the underlying maternal condition.

8.4 Pediatric Use

Acthar Gel is indicated as monotherapy for the treatment of infantile spasms in infants and children less than 2 years of age. Both serious and other adverse reactions can occur in this population [see Warnings and Precautions (5) and Adverse Reactions (6.1)].

The efficacy of Acthar Gel for the treatment of infantile spasms in infants and children less than 2 years of age was evaluated in a randomized, single blinded (video EEG interpreter blinded) clinical trial and an additional active control supportive trial [see Clinical Studies (14)]. A responding patient was defined as having both complete cessation of spasms and elimination of hypsarrhythmia.

Safety in the pediatric population for infantile spasms was evaluated by retrospective chart reviews and data from non-sponsor conducted clinical trials [see Adverse Reactions (6.1)]. While the types of adverse reactions seen in infants and children under 2 years of age treated for infantile spasms are similar to those seen in older patients, their frequency and severity may be different due to the very young age of the infant, the underlying disorder, the duration of therapy and the dosage regimen. Effects on growth are of particular concern [see Warnings and Precautions (5.12)]. Serious adverse reactions observed in adults may also occur in children [see Warnings and Precautions (5)].

11 DESCRIPTION

Acthar Gel is a naturally sourced complex mixture of adrenocorticotropic hormone analogs and other pituitary peptides. The Acthar Gel manufacturing process converts the initial porcine pituitary extract with low ACTH content into a mixture having modified porcine ACTH and other related peptide analogs solubilized in gelatin. A major component in the formulated complex mixture is N-25 deamidated porcine ACTH (1-39).

Acthar Gel is supplied as a sterile preparation in 16% gelatin to provide a prolonged release after intramuscular or subcutaneous injection. Acthar Gel also contains 0.5% phenol, not more than 0.1% cysteine (added), sodium hydroxide and/or acetic acid to adjust pH and Water for Injection.

12 CLINICAL PHARMACOLOGY

12.1 Mechanism of Action

The mechanism of action of Acthar Gel in the treatment of infantile spasms is unknown.

Acthar Gel and endogenous ACTH stimulate the adrenal cortex to secrete cortisol, corticosterone, aldosterone, and a number of weakly androgenic substances. Prolonged administration of large doses of Acthar Gel induces hyperplasia and hypertrophy of the adrenal cortex and continuous high output of cortisol, corticosterone and weak androgens. The release of endogenous ACTH is under the influence of the nervous system via the regulatory hormone released from the hypothalamus and by a negative corticosteroid feedback mechanism. Elevated plasma cortisol suppresses ACTH release.

Acthar Gel is also reported to bind to melanocortin receptors.

The trophic effects of endogenous ACTH and Acthar Gel on the adrenal cortex are not well understood beyond the fact that they appear to be mediated by cyclic AMP.

12.3 Pharmacokinetics

ACTH rapidly disappears from the circulation following its intravenous administration; in people, the plasma half-life is about 15 minutes. The pharmacokinetics of Acthar Gel have not been adequately characterized.

The maximal effects of a trophic hormone on a target organ are achieved when optimal amounts of hormone are acting continuously. Thus, a fixed dose of Acthar Gel will demonstrate a linear increase in adrenocortical secretion with increasing duration for the infusion.

13 NONCLINICAL TOXICOLOGY

13.1 Carcinogenesis, Mutagenesis, Impairment of Fertility

Carcinogenesis

Adequate studies of the carcinogenic potential of Acthar Gel have not been conducted.

Mutagenesis

The genotoxic potential of Acthar Gel has not been adequately evaluated.

Impairment of Fertility

The potential effects of Acthar Gel on fertility have not been adequately assessed in animals.

14 CLINICAL STUDIES

The effectiveness of Acthar Gel as a treatment for infantile spasms was demonstrated in a single blinded (video EEG interpreter blinded) clinical trial in which patients were randomized to receive either a 2-week course of treatment with Acthar Gel (75 U/m^2 intramuscular twice daily) or prednisone (1 mg/kg by mouth twice daily). The primary outcome was a comparison of the number of patients in each group who were treatment responders, defined as a patient having complete suppression of both clinical spasms and hypsarrhythmia on a full sleep cycle video EEG performed 2 weeks following treatment initiation, rated by an investigator blinded to treatment. Thirteen of 15 patients (86.7%) responded to Acthar Gel as compared to 4 of 14 patients (28.6%) given prednisone (p<0.002). The 2-week treatment was followed by a 2-week period of taper. Nonresponders to the prednisone treatment were eligible to receive Acthar Gel treatment. Seven of 8 patients (87.5%) responded to Acthar Gel after not responding to prednisone. Similarly, the 2 nonresponder patients from the Acthar Gel treatment were eligible to receive treatment with prednisone. One of the 2 patients (50%) responded to the prednisone treatment after not responding to Acthar Gel.

A supportive single-blind, randomized clinical trial comparing high-dose, long-duration treatment (150 U/m^2 once daily for 3 weeks, n=30) of Acthar Gel with low-dose, short-duration treatment (20 U once daily for 2 weeks, n=29) for the treatment of infantile spasms was also evaluated in infants and children less than 2 years of age. Nonresponders (defined as in the previously described study) in the low-dose group received a dose escalation at 2 weeks to 30 U once daily. Nominal statistical superiority of the high dose treatment, as compared to the low dose treatment, was observed for cessation of spasms but not for the resolution of hypsarrhythmia.

16 HOW SUPPLIED/STORAGE AND HANDLING

16.1 How Supplied

Acthar Gel (repository corticotropin injection) is a clear light amber solution mobile at room temperature. Acthar Gel is supplied in the following configurations:

Strength | Package size | NDC number
80 USP Units/mL | 5 mL multi-dose vial (1 count) | 63004-8710-1
40 USP Units/0.5 mL | Single-dose pre-filled SelfJect injector (4 count) | 63004-8712-4
80 USP Units/mL | Single-dose pre-filled SelfJect injector (4 count) | 63004-8711-4

16.2 Storage and Handling

Store Acthar Gel vial and Acthar Gel single-dose pre-filled SelfJect injector under refrigeration between 2°C to 8°C (36°F to 46°F) in the carton to protect from light.

After removing the single-dose pre-filled SelfJect injector from the refrigerator, it can be stored at room temperature between 20°C to 25°C (68°F to 77°F) for up to 24 hours. Do not heat, freeze, or put the Acthar Gel single-dose pre-filled SelfJect injector into direct sunlight.

Dispense single-dose pre-filled SelfJect injectors in the original sealed carton with the enclosed Instructions for Use.

17 PATIENT COUNSELING INFORMATION

Advise caretakers of patients with infantile spasms to read the FDA-approved patient labeling (Medication Guide [for infantile spasms]).

Advise caretakers or patients 18 years of age or older to read the FDA-approved Instructions for Use when administering Acthar Gel single-dose pre-filled SelfJect injector.

Use and Monitoring

Patients should be instructed to take Acthar Gel only as prescribed. They should not stop treatment suddenly unless instructed by their healthcare provider to do so.

Patients, their caregivers and families should be advised as to the importance of the need for careful monitoring while on and during titration from Acthar Gel treatment and the importance of not missing scheduled doctor's appointments.

Infections

Advise patients, their caregivers, and families to contact their healthcare provider if the patient develops an infection or fever. Inform patients and caregivers that a fever may not necessarily be present during infection and to try to limit contact with other people with infections to minimize the risk of infection while taking Acthar Gel [see Warnings and Precautions (5.1) and Adverse Reactions (6.1)].

Cushing's Syndrome and Adrenal Insufficiency Upon Withdrawal

Advise patients to contact their healthcare provider if they develop signs or symptoms of Cushing's Syndrome, such as fat increases in the face (moon face) or trunk area, cutaneous striae, easy bruisability, weight gain, muscle weakness, hyperglycemia, and hypertension [see Warnings and Precautions (5.2)].

Inform patients that adrenal insufficiency can occur upon withdrawal of Acthar Gel. Advise patients to contact their healthcare provider if they develop weakness, hyperpigmentation, weight loss, hypotension, or abdominal pain. Advise caregivers of patients with infantile spasms that symptoms of adrenal insufficiency may be difficult to identify and that additional symptoms may include anorexia, fatigue, or lethargy [see Warnings and Precautions (5.2)].

Elevated Blood Pressure, Salt and Water Retention, and Hypokalemia

Advise patients, their caregivers and families to contact their healthcare provider if the patient experiences an increase in blood pressure or water retention [see Warnings and Precautions (5.3) and Adverse Reactions (6.1)].

Vaccinations

Advise patients and caregivers of patients to not to be vaccinated with live or live attenuated vaccines during treatment with Acthar Gel. Additionally, other immunization procedures in patients or in family members who will be in contact with the patient should be undertaken with caution while the patient is taking Acthar Gel [see Warnings and Precautions (5.4)].

Masking Symptoms of Other Diseases

Inform patients, their caregivers, and families that Acthar Gel may mask symptoms of other diseases/disorders without altering the course of the other disease/disorder. Monitor the patient carefully during and for a period following discontinuation of therapy and inform their healthcare provider if signs of infection, abnormal cardiac function, hypertension, hyperglycemia, change in body weight, or fecal blood loss occur [see Warnings and Precautions (5.5)].

Gastrointestinal Perforation and Bleeding

Advise patients, their caregivers and families to contact their healthcare provider if the patient or the caregiver notices blood or a change in color of the patient's stool [see Warnings and Precautions (5.6)].

Behavioral and Mood Disturbances

Inform patients, their caregivers and families that signs of irritability, sleep disturbances, mood swings, personality changes, or severe depression may occur. These effects are reversible once Acthar Gel therapy is stopped [see Warnings and Precautions (5.7) and Adverse Reactions (6.1)].

Negative Effects on Growth and Physical Development

Advise patients, their caregivers and families that changes in appetite, most often leading to weight gain, are seen with Acthar Gel therapy, becoming more frequent as the dose or treatment period increases. These effects are reversible once Acthar Gel therapy is stopped [see Warnings and Precautions (5.12) and Adverse Reactions (6.1)].

Decrease in Bone Density

Advise patients, their caregivers and families that prolonged use of Acthar Gel may inhibit skeletal growth in children and adolescents and may cause osteoporosis and decreased bone density at any age. If prolonged use is necessary, Acthar Gel should be given intermittently along with careful observation [see Warnings and Precautions (5.13) and Adverse Reactions (6.1)].

Infantile Spasms Additional Information

Inform caregivers that, in the treatment of infantile spasms, other types of seizures may occur because some patients with infantile spasms progress to other forms of seizures (for example, Lennox-Gastaut Syndrome). Additionally, the spasms sometimes mask other seizures and once the spasms resolve after treatment with Acthar Gel, the other seizures may become visible. Advise parents and caregivers to inform the patient's healthcare provider of any new onset of seizures so that appropriate management can then be instituted [see Adverse Reactions (6.1)].

Pregnancy

Advise pregnant women of the potential risk to a fetus [see Use in Specific Populations (8.1)].

Mallinckrodt, the "M" brand mark, SelfJect, the Mallinckrodt Pharmaceuticals logo and other brands are trademarks of a Mallinckrodt company. © 2024 Mallinckrodt.

For a list of patents, see https://www.mallinckrodt.com/patents/

Manufactured for:
Mallinckrodt ARD LLC
Bridgewater, NJ 08807

SPC-0188 Rev 3

Mallinckrodt™
Pharmaceuticals

MEDICATION GUIDE

Acthar® Gel (AK-thar jel)
(repository corticotropin injection)

This Medication Guide provides information only about the use of Acthar Gel for the treatment of Infantile Spasms. If your doctor prescribes Acthar Gel for you or your child for any other reason, talk to your doctor for information about how this medicine is used to treat your medical condition.

Read this Medication Guide before your child receives Acthar Gel and each time you refill your child's prescription. There may be new information. This Medication Guide does not take the place of talking with your doctor about your child's medical condition or treatment.

What is the most important information I should know about Acthar Gel?

Acthar Gel can cause serious side effects including:

1. Increased risk of infections.
  Acthar Gel is a medicine that can affect your child's immune system. When your child is taking Acthar Gel, it can lower the ability of your child's immune system to fight infections.
  Acthar Gel may:
  - make your child more likely to get new infections
  - worsen an infection that your child already has
  - cause an inactive infection to become active, such as tuberculosis (TB)
  Before starting Acthar Gel, tell your doctor if your child has:
  - an infection or signs of an infection, such as:
    - fever
    - cough
    - vomiting
    - diarrhea
    - other signs of flu or illness
  - a family member with an infection or signs of an infection
  While taking Acthar Gel, your child should:
  - stay away from people who are sick or who have infections
  - tell your doctor right away if your child has any sign of infection such as:
    - fever (but your child may not have a fever with an infection)
    - cough
    - vomiting
    - diarrhea or
    - other signs of illness or flu and
    - any open cuts or sores on his or her body
2. Effects on the adrenal gland after stopping Acthar Gel.
  When your child stops taking Acthar Gel, his or her body may not produce enough of a hormone called cortisol on its own (adrenal insufficiency). Your child may need to take steroid medicine to protect the body until the adrenal gland recovers and is working well again, especially to protect the body if they have surgery or trauma. Do not stop giving your child injections of Acthar Gel without talking to your doctor first.
  Your doctor will tell you when and how to slowly stop giving the injections to avoid serious side effects.
  While slowly stopping your child's injections of Acthar Gel or after you stop giving the injections, call your doctor right away if your child has any of the following:
  - appears weak
  - loses weight or has a decrease in appetite
  - appears tired or lacking energy
  - appears pale
  - has stomach pain
  - appears sick or is with a fever
3. Effects on the adrenal gland while taking Acthar Gel.
  When your child is taking Acthar Gel, his or her adrenal gland may produce too much cortisol. This can cause symptoms of Cushing's syndrome. Cushing's syndrome is more common in children who take Acthar Gel for a long time.
  Symptoms of Cushing's syndrome include:
  - increased upper body fat around the neck, but not the arms and legs
  - weight gain
  - rounded or "moon" face
  - thin skin, easy bruising, and stretch marks on thighs, belly and trunk
  - slowed growth rates in children
  - weak bones (osteoporosis)
  While receiving treatment with Acthar Gel other side effects can happen that are like side effects that happen due to treatment with steroid medicines. The risk of getting side effects may increase the longer your child is treated with Acthar Gel. Side effects may include:
  - increased blood pressure. Your doctor may check your child's blood pressure during treatment. If your child's blood pressure increases, your doctor may talk with you about possible treatment choices.
  - too much water in the body (water retention), increased amount of body salts, and low potassium in the blood. Acthar Gel may cause your child to have an increased amount of body salts and water that stays in the body, and may lower the amount of potassium in your child's blood. Follow your doctor's instructions about if you need to decrease your child's salt intake or if you need to feed your child foods high in potassium.
4. Your child should not receive certain vaccines during treatment with Acthar Gel.
  Your child may receive killed or inactivated vaccines while receiving Acthar Gel. Before your child receives any vaccines, talk to your doctor about which vaccines are safe for your child. Certain vaccines could cause your child to have serious side effects, or the vaccine may not be effective.
5. Hiding (masking) symptoms of other conditions or diseases.
  It may be more difficult for your doctor to diagnose other conditions or diseases in your child during treatment with Acthar Gel. During treatment and after treatment ends, tell your doctor if your child has:
  - any signs or symptoms of infection. See number 1 of this section in the Medication Guide.
  - changes in body weight
  - bloody or black tarry stool
  - vomiting
  - stomach pain
  - excessive tiredness
  - increased thirst
  - fast heart rate
  - difficulty breathing
6. Stomach and intestinal problems. Acthar Gel may cause bleeding of the stomach or intestine.
  Your child has an increased risk for bleeding from the stomach or having a stomach ulcer. Tell your doctor if your child has any pain in the stomach area (abdominal pain), vomits blood, or has bloody or black stools.
7. Changes in mood and behavior.
  During treatment with Acthar Gel your child may be irritable, have rapid changes in his or her mood, be depressed, have other changes in his or her behavior, or have trouble sleeping.
  Tell your doctor if your child has any of the side effects or symptoms listed above.

What is Acthar Gel?

Acthar Gel is a prescription medicine that is used to treat infantile spasms in infants and children under 2 years of age.

What should I tell my doctor before my child takes Acthar Gel?

Before your child takes Acthar Gel, read the section above "What is the most important information I should know about Acthar Gel?" and tell your doctor if your child has:

- an infection
- diabetes
- heart problems
- kidney problems
- stomach or intestinal problems
- thyroid problems
- liver problems
- neuromuscular problems
- convulsions or seizures
- had exposure to someone with Tuberculosis (TB)
- a previous allergic reaction such as hives, itching or trouble breathing, to Acthar Gel or pork products
- had recent surgery
- had a recent vaccination or is scheduled to receive a vaccination
- a family member who is receiving vaccinations

Tell your doctor about all the medicines your child takes, including prescription and non- prescription medicines, vitamins and herbal supplements. Do not start giving a new medicine to your child without first speaking to your doctor.

How should I give Acthar Gel to my child?

Acthar Gel is given as an injection into the muscle. Do not inject it under the skin, into a vein, or give it to your child by mouth.

- Inject Acthar Gel exactly as your doctor tells you. Your doctor will tell you where to give the injection, how much to give, how often and when to give it to your child.
- Do not use Acthar Gel until your doctor has taught you how to give the injection to your child.
- To give Acthar Gel:
  - Take the bottle from the refrigerator. Do not open the bottle or pry the cap (rubber stopper) off.
  - Warm the contents by rolling the bottle between your hands for a few minutes.
  - Wash your hands.
  - Prepare the skin where you are going to give the injection by wiping it with a new sterile alcohol wipe. Before giving the injection, look at the site prepared for the injection and make sure that it no longer looks wet. A wet site can cause burning.
  - Wipe the top of the vial rubber stopper with a new sterile alcohol wipe.
  - Use a new sterile needle and syringe to draw up the amount of Acthar Gel the doctor has told you to use.
  - Give the injection the way the doctor has instructed you.
  - Return the bottle to the refrigerator as soon as possible.

Keep all of your child's follow-up appointments with your doctor

- It is important for you to tell your doctor if your child's spasms continue or change in any way during treatment or after treatment has stopped so that they can monitor your child's progress.

Infantile Spasms sometimes hides (masks) other seizures your child or infant may have. Once treated with Acthar Gel, the Infantile Spasms symptoms may disappear. This may allow the other seizures to become visible for the first time. Tell your child's doctor right away if you see a change in your child's seizures/spasms.

What are the possible side effects of Acthar Gel?

Acthar Gel can cause serious side effects.

- See "What is the most important information I should know about Acthar Gel."
- Acthar Gel may make certain other medical conditions worse, such as diabetes (may increase blood sugar).
- Eye problems. Your child can get cataracts, increased pressure in the eye (glaucoma), and possible damage to the optic nerve if treated with Acthar Gel for a long time.
- Allergic reactions to Acthar Gel. Your child may have an allergic reaction to Acthar Gel. Allergic reactions may not happen until your child has received several injections of Acthar Gel. Tell your doctor right away if your child has any of the following signs of an allergic reaction:
  - skin rash
  - swelling of the face, tongue, lips, or throat
  - trouble breathing
- Changes in growth and physical development. Acthar Gel may affect your child's growth and physical development and may weaken his or her bones. This is more likely to happen with long term use of Acthar Gel.
- Enlarged heart. Acthar Gel may cause an increase in the size of your child's heart. This is more likely to happen with long term use of Acthar Gel but usually goes away after Acthar Gel is stopped.

The most common side effects of Acthar Gel for patients with infantile spasms include:

- Infections
- muscle contractions that you cannot control (convulsions)
- increased blood pressure
- irritability and changes in behavior
- fever

These are not all the possible side effects of Acthar Gel. Tell your doctor if your child has any side effect that bothers them or does not go away. For more information, ask your child's doctor or pharmacist.

Call your doctor for medical advice about side effects. You may report side effects to FDA at 1-800-FDA-1088.

How should I store Acthar Gel?

- Store vials of Acthar Gel in the refrigerator between 36°F to 46°F (2°C to 8°C).

Throw away any vials after the expiration date printed on the label.

Keep Acthar Gel and all other medicines out of the reach of children

General information About Acthar Gel

Medicines are sometimes prescribed for purposes other than those listed in a Medication Guide. Do not use Acthar Gel for a condition for which it has not been prescribed. Do not give Acthar Gel to other people, even if they have the same symptoms. It may harm them.

This Medication Guide summarizes the most important information about Acthar Gel. If you would like more information, talk with your child's doctor. You can ask your child's doctor or pharmacist for information about Acthar Gel that is written for healthcare professionals. For more information, go to www.acthar.com or call 1-800-844-2830.

What are the ingredients in Acthar Gel?

Active ingredient: Corticotropin
Inactive ingredients: gelatin, phenol, cysteine, sodium hydroxide and/or acetic acid to adjust pH, and water for injection

Manufactured for:

Mallinckrodt ARD LLC
Bridgewater, NJ 08807

PL122
Rev 02/2024

This Medication Guide has been approved by the U.S. Food and Drug Administration.

Mallinckrodt, the "M" brand mark, the Mallinckrodt Pharmaceuticals logo and other brands are trademarks of a Mallinckrodt company. © 2024 Mallinckrodt.

For a list of patents, see https://www.mallinckrodt.com/patents/

Mallinckrodt™
Pharmaceuticals

INSTRUCTIONS FOR USE

ACTHAR® GEL [AK-thar jel]
(repository corticotropin injection)
for subcutaneous use only
Single-Dose Pre-filled SelfJect™ Injector

Green Body Injector: 40 USP Units/0.5 mL of Acthar Gel

Step 1: Read These Instructions

- Carefully read, understand, and follow this Instructions for Use before you use the Acthar Gel single-dose pre-filled SelfJect injector.
- Contact your healthcare provider if you are unsure of how to give the injection.

Important Information

- The Acthar Gel single-dose pre-filled SelfJect injector is for under the skin (subcutaneous) injection only.
- The Acthar Gel single-dose pre-filled SelfJect injector must only be given by adults 18 years of age and older.
- The Acthar Gel single-dose pre-filled SelfJect injector is a pre-filled injector for 1-time use only (single-dose).
- The Acthar Gel single-dose pre-filled SelfJect injector with the green body should only be used to give a single dose of 40 units. Doses other than 40 units cannot be given with this Acthar Gel single-dose pre-filled SelfJect injector.
- This injector is not an auto-injector. The Handle must be pushed down by hand (see "The parts of the Acthar Gel single-dose pre-filled SelfJect injector" figure below).
- The injector has a Needle Guard to protect you and others from injury after it has been used.

The parts of the Acthar Gel single-dose pre-filled SelfJect injector are shown below:

Before Use

After the Injection is Complete

Storing Your Injector

- Store the Acthar Gel single-dose pre-filled SelfJect injector in the refrigerator between 36°F and 46°F (2°C and 8°C).
- Store the Acthar Gel single-dose pre-filled SelfJect injector in the original plastic tray to protect the injector from light.
- When it is time to use the Acthar Gel single-dose pre-filled SelfJect injector, take 1 injector from the refrigerator and return any unused injectors to the refrigerator.
- After removing the injector from the refrigerator, it can be stored at room temperature between 68°F and 77°F (20°C and 25°C) for up to 24 hours.
- If the Acthar Gel single-dose pre-filled SelfJect injector has been left at room temperature for more than 24 hours, contact Mallinckrodt: 1-800-844-2830.
- Do not heat the Acthar Gel single-dose pre-filled SelfJect injector.
- Do not freeze the Acthar Gel single-dose pre-filled SelfJect injector.
- Do not put the Acthar Gel single-dose pre-filled SelfJect injector into direct sunlight.
- Keep the Acthar Gel single-dose pre-filled SelfJect injector and all medicines out of the reach of children.

Step 2: Prepare to Use the Acthar Gel single-dose pre-filled SelfJect injector

- Choose a clean, well-lit room to give the injection.

- Take the injector tray out of the refrigerator.
- If the injector trays are in a multipack carton, take the injector tray out and return any unused injector trays to the refrigerator.
- Do not inject Acthar Gel right after removing it from the refrigerator. The injector does not work as well when cold.

- Check that you have the correct medicine and dose.
- Check the expiration date (EXP) on the package.
  Do not use if the expiration date has passed.

- Remove the injector from the injector tray and let it sit on a clean, dry, flat surface at room temperature to warm for a minimum of 45 minutes and no more than 24 hours before use.
  Do not heat the injector.

- Before use, the injector should look like this.
- The Bottom Cap should remain on the injector until you give the injection.

- Do not use the injector if the Bottom Cap is missing or not securely attached.
- If dropped, inspect the injector. Do not use if the injector is damaged or the Bottom Cap has come off.

- Gather an alcohol swab and sharps disposal container.
- You may also gather an adhesive bandage, gauze, or cotton ball to use after the injection to stop any bleeding.

Step 3: Choose and Clean the Injection Site

- The Acthar Gel single-dose pre-filled SelfJect injector is for under the skin (subcutaneous) injection only.
- Choose 1 of these sites for injection:
  - Upper thigh
  - Belly (abdomen), not within 1-inch of belly button (navel)
  - Back of arm (only if someone else is giving the injection)

- Choose a different site for each injection. Do not use the same injection site more than 1 time each week.
- Do not inject through clothing.
- Avoid injecting into:
  - Irritated skin (red, swollen, or painful)
  - Tattoos
  - Warts
  - Scars
  - Birthmarks
  - Within 1-inch of the knee
  - Within 1-inch of the groin area
  - Stretch marks

- Wash your hands well with soap and water.

- Clean the injection site with an alcohol swab.
- Do not touch, fan, or blow on the injection site after you have cleaned it.

Step 4: Inspect and Uncap

- Make sure the injector has warmed at room temperature for a minimum of 45 minutes before you continue.
- Inspect the medicine in the Window.
- If needed, wipe away any condensation (water collected) from the Window with a dry cloth.
- Check the medicine in the Window. It should be a clear light yellow or orange solution.
- Do not use if the medicine is cloudy or you see particles.
- Note: It is normal to see air bubbles.

- Pull the Bottom Cap off to remove it and throw it away in your household trash.
- Avoid touching the Gray Needle Guard. The injector is now ready for use.
- After the injector has been warmed for a minimum of 45 minutes and you have prepared the injection site, use the injector right away.
  Do not recap the injector as this may damage the needle.

- When the Bottom Cap is removed, do not let the Gray Needle Guard touch any surface before injection.

Step 5: Inject

- Place the injector straight on the cleaned skin at a 90-degree angle.
  Do not pinch the skin.

- Slowly push the Handle down to inject the medicine.
  Do not lift the injector during the injection. If you do, the injector will lock out and you will not get the full dose of medicine.
  You may hear a "click" when the injection begins.

- The injection is complete when the Green Colored Body disappears and you may hear a "click".

Before you lift the injector up, check to make sure that no part of the Green Colored Body remains visible. If you see color, continue pushing down on the Handle until the Green Colored Body disappears completely.

Step 6: Lift

- Lift the injector straight up at a 90-degree angle off the injection site.
  If the Yellow Band is visible, it means that the Needle Guard is locked. You cannot use the injector again.

After the injection is complete, the injector should look like this:

After use, the injector should not look like this:

If you see the Green Colored Body and the Yellow Band at the same time, then you did not give the full dose.
Do not try to inject with this injector again.
Do not use another injector. Contact your healthcare provider.

- If there is any bleeding at the injection site, cover the site with an adhesive bandage, a cotton ball, or a gauze. Apply gentle pressure until the bleeding stops.

Step 7: Throw Away (Dispose of) your Used Acthar Gel single-dose pre-filled SelfJect injector

- Put your used Acthar Gel single-dose pre-filled SelfJect injector in an FDA-cleared sharps disposal container right away after use.
- Do not throw away your injector in your household trash.
- If you do not have an FDA-cleared sharps disposal container, you may use a household container that is:
  - made of a heavy-duty plastic,
  - can be closed with a tight-fitting, puncture-resistant lid, without sharps being able to come out,
  - upright and stable during use,
  - leak-resistant, and
  - properly labelled to warn of hazardous waste inside the container.

- When your sharps disposal container is almost full, you will need to follow your community guidelines for the right way to dispose of your sharps disposal container. There may be state or local laws about how you should throw away used needles and syringes. For more information about safe sharps disposal, and for specific information about sharps disposal in the state that you live in, go to the FDA's website at: http://www.fda.gov/safesharpsdisposal
- Do not dispose of your used sharps disposal container in your household trash unless your community guidelines permit this.
- Do not recycle your used sharps disposal container.

Manufactured for:
Mallinckrodt ARD LLC
Bridgewater, NJ 08807

SPC-0204 Rev 8

This Instructions for Use has been approved by the U.S. Food and Drug Administration.

Revised: 08/2024

Quick Reference Guide

ACTHAR® GEL [AK-thar jel]
(repository corticotropin injection)
for subcutaneous use only
40 USP Units/0.5 mL
Single-Dose Pre-filled SelfJect™ Injector

Before use

After the Injection is Complete

Important Information

- The Acthar Gel single-dose pre-filled SelfJect injector is for under the skin (subcutaneous) injection only.

1. Read These Instructions

- Contact your healthcare provider if you are unsure of how to give the injection.
- This is not an auto-injector. The Handle must be pushed down by hand.
- This is a single-dose injector (for 1-time use only).
- The injector has a Needle Guard to protect you after use.

2. Prepare to Use the Acthar Gel single-dose pre-filled SelfJect Injector

- Take the injector out of the refrigerator and remove it from its injector tray to warm at room temperature for a minimum of 45 minutes.

- Do not use the injector right after removing from the refrigerator. The injector does not work as well when cold. Do not heat.
- Check the expiration date (EXP) on the package.
- Complete this injection in a clean, well-lit room.
- Gather alcohol swab, adhesive bandage, and a sharps disposal container.

3. Choose and Clean the Injection Site

- For under the skin (subcutaneous) injection only. - Choose 1 of these sites for injection: - Upper thigh - Belly (abdomen), not within 1-inch of belly button (navel) - Back of arm (only if someone else is giving the injection) - Choose a different site for each injection. - Do not inject through clothing. - Avoid injecting into: - Irritated skin (red, swollen, or painful) - Tattoos, warts, scars, or birthmarks - Within 1-inch of knee or groin area - Stretch marks |  | - Wash your hands well with soap and water.
- For under the skin (subcutaneous) injection only. - Choose 1 of these sites for injection: - Upper thigh - Belly (abdomen), not within 1-inch of belly button (navel) - Back of arm (only if someone else is giving the injection) - Choose a different site for each injection. - Do not inject through clothing. - Avoid injecting into: - Irritated skin (red, swollen, or painful) - Tattoos, warts, scars, or birthmarks - Within 1-inch of knee or groin area - Stretch marks |  | - Clean the injection site with an alcohol swab.

4. Inspect and Uncap

- Inspect the medicine in the Window. The medicine should be a clear light yellow or orange solution.
- Do not use if the medicine is cloudy or you see particles.
- It is normal to see air bubbles.

Pull Bottom Cap off to remove it and throw it away.

- Do not recap the injector as this may damage the needle.
- Avoid touching the Gray Needle Guard.
- Use the injector right away.

5. Inject

(a) Place the injector straight on the cleaned skin at a 90-degree angle. Do not pinch the skin. | (b) Slowly push down the Handle to inject the medicine. Do not lift the injector during the injection. You may hear a "click" when the injection begins. | (c) The injection is complete when the Green Colored Body disappears and you may hear a "click."

6. Lift and Throw Away (Dispose of)

Lift the injector straight up at a 90-degree angle off the injection site.
The Needle Guard is locked when you see the yellow band.

Place the injector in an approved sharps disposal container according to local regulations.
Do not throw away (dispose of) in your household trash.
SPC-0131 Rev 9

INSTRUCTIONS FOR USE

ACTHAR® GEL [AK-thar jel]
(repository corticotropin injection)
for subcutaneous use only
Single-Dose Pre-filled SelfJect™ Injector

Purple Body Injector: 80 USP Units/mL of Acthar Gel

Step 1: Read These Instructions

- Carefully read, understand, and follow this Instructions for Use before you use the Acthar Gel single-dose pre-filled SelfJect injector.
- Contact your healthcare provider if you are unsure of how to give the injection.

Important Information

- The Acthar Gel single-dose pre-filled SelfJect injector is for under the skin (subcutaneous) injection only.
- The Acthar Gel single-dose pre-filled SelfJect injector must only be given by adults 18 years of age and older.
- The Acthar Gel single-dose pre-filled SelfJect injector is a pre-filled injector for 1-time use only (single-dose).
- The Acthar Gel single-dose pre-filled SelfJect injector with the purple body should only be used to give a single dose of 80 units. Doses other than 80 units cannot be given with this Acthar Gel single-dose pre-filled SelfJect injector.
- This injector is not an auto-injector. The Handle must be pushed down by hand (see "The parts of the Acthar Gel single-dose pre-filled SelfJect injector" figure below).
- The injector has a Needle Guard to protect you and others from injury after it has been used.

The parts of the Acthar Gel single-dose pre-filled SelfJect injector are shown below:

Before Use

After the Injection is Complete

Storing Your Injector

- Store the Acthar Gel single-dose pre-filled SelfJect injector in the refrigerator between 36°F and 46°F (2°C and 8°C).
- Store the Acthar Gel single-dose pre-filled SelfJect injector in the original plastic tray to protect the injector from light.
- When it is time to use the Acthar Gel single-dose pre-filled SelfJect injector, take 1 injector from the refrigerator and return any unused injectors to the refrigerator.
- After removing the injector from the refrigerator, it can be stored at room temperature between 68°F and 77°F (20°C and 25°C) for up to 24 hours.
- If the Acthar Gel single-dose pre-filled SelfJect injector has been left at room temperature for more than 24 hours, contact Mallinckrodt: 1-800-844-2830.
- Do not heat the Acthar Gel single-dose pre-filled SelfJect injector.
- Do not freeze the Acthar Gel single-dose pre-filled SelfJect injector.
- Do not put the Acthar Gel single-dose pre-filled SelfJect injector into direct sunlight.
- Keep the Acthar Gel single-dose pre-filled SelfJect injector and all medicines out of the reach of children.

Step 2: Prepare to Use the Acthar Gel single-dose pre-filled SelfJect injector

- Choose a clean, well-lit room to give the injection.

- Take the injector tray out of the refrigerator.
- If the injector trays are in a multipack carton, take the injector tray out and return any unused injector trays to the refrigerator.
- Do not inject Acthar Gel right after removing it from the refrigerator. The injector does not work as well when cold.

- Check that you have the correct medicine and dose.
- Check the expiration date (EXP) on the package.
  Do not use if the expiration date has passed.

- Remove the injector from the injector tray and let it sit on a clean, dry, flat surface at room temperature to warm for a minimum of 45 minutes and no more than 24 hours before use.
  Do not heat the injector.

- Before use, the injector should look like this.
- The Bottom Cap should remain on the injector until you give the injection.

- Do not use the injector if the Bottom Cap is missing or not securely attached.
- If dropped, inspect the injector. Do not use if the injector is damaged or the Bottom Cap has come off.

- Gather an alcohol swab and sharps disposal container.
- You may also gather an adhesive bandage, gauze, or cotton ball to use after the injection to stop any bleeding.

Step 3: Choose and Clean the Injection Site

- The Acthar Gel single-dose pre-filled SelfJect injector is for under the skin (subcutaneous) injection only.

- Choose 1 of these sites for injection:
  - Upper thigh
  - Belly (abdomen), not within 1-inch of belly button (navel)
  - Back of arm (only if someone else is giving the injection)

- Choose a different site for each injection. Do not use the same injection site more than 1 time each week.
- Do not inject through clothing.
- Avoid injecting into:
  - Irritated skin (red, swollen, or painful)
  - Tattoos
  - Warts
  - Scars
  - Birthmarks
  - Within 1-inch of the knee
  - Within 1-inch of the groin area
  - Stretch marks

- Wash your hands well with soap and water.

- Clean the injection site with an alcohol swab.
- Do not touch, fan, or blow on the injection site after you have cleaned it.

Step 4: Inspect and Uncap

- Make sure the injector has warmed at room temperature for a minimum of 45 minutes before you continue.
- Inspect the medicine in the Window.
- If needed, wipe away any condensation (water collected) from the Window with a dry cloth.
- Check the medicine in the Window. It should be a clear light yellow or orange solution.
- Do not use if the medicine is cloudy or you see particles.
- Note: It is normal to see air bubbles.

- Pull the Bottom Cap off to remove it and throw it away in your household trash.
- Avoid touching the Gray Needle Guard. The injector is now ready for use.
- After the injector has been warmed for a minimum of 45 minutes and you have prepared the injection site, use the injector right away.
  Do not recap the injector as this may damage the needle.

- When the Bottom Cap is removed, do not let the Gray Needle Guard touch any surface before injection.

Step 5: Inject

- Place the injector straight on the cleaned skin at a 90-degree angle.
  Do not pinch the skin.

- Slowly push the Handle down to inject the medicine.
  Do not lift the injector during the injection. If you do, the injector will lock out and you will not get the full dose of medicine.
  You may hear a "click" when the injection begins.

- The injection is complete when the Purple Colored Body disappears and you may hear a "click".

Before you lift the injector up, check to make sure that no part of the Purple Colored Body remains visible. If you see color, continue pushing down on the Handle until the Purple Colored Body disappears completely.

Step 6: Lift

- Lift the injector straight up at a 90-degree angle off the injection site.
  If the Yellow Band is visible, it means that the Needle Guard is locked. You cannot use the injector again.

After the injection is complete, the injector should look like this:

After use, the injector should not look like this:

If you see the Purple Colored Body and the Yellow Band at the same time, then you did not give the full dose.
Do not try to inject with this injector again.
Do not use another injector. Contact your healthcare provider.

- If there is any bleeding at the injection site, cover the site with an adhesive bandage, a cotton ball, or a gauze. Apply gentle pressure until the bleeding stops.

Step 7: Throw Away (Dispose of) your Used Acthar Gel single-dose pre-filled SelfJect injector

- Put your used Acthar Gel single-dose pre-filled SelfJect injector in an FDA-cleared sharps disposal container right away after use.
- Do not throw away your injector in your household trash.
- If you do not have an FDA-cleared sharps disposal container, you may use a household container that is:
  - made of a heavy-duty plastic,
  - can be closed with a tight-fitting, puncture-resistant lid, without sharps being able to come out,
  - upright and stable during use,
  - leak-resistant, and
  - properly labelled to warn of hazardous waste inside the container.

- When your sharps disposal container is almost full, you will need to follow your community guidelines for the right way to dispose of your sharps disposal container. There may be state or local laws about how you should throw away used needles and syringes. For more information about safe sharps disposal, and for specific information about sharps disposal in the state that you live in, go to the FDA's website at: http://www.fda.gov/safesharpsdisposal
- Do not dispose of your used sharps disposal container in your household trash unless your community guidelines permit this.
- Do not recycle your used sharps disposal container.

Manufactured for:
Mallinckrodt ARD LLC
Bridgewater, NJ 08807

SPC-0205 Rev 8

This Instructions for Use has been approved by the U.S. Food and Drug Administration.

Revised: 08/2024

Quick Reference Guide

ACTHAR® GEL [AK-thar jel]
(repository corticotropin injection)
for subcutaneous use only
80 USP Units/mL
Single-Dose Pre-filled SelfJect™ Injector

Before use

After the Injection is Complete

Important Information

- The Acthar Gel single-dose pre-filled SelfJect injector is for under the skin (subcutaneous) injection only.

1. Read These Instructions

- Contact your healthcare provider if you are unsure of how to give the injection.
- This is not an auto-injector. The Handle must be pushed down by hand.
- This is a single-dose injector (for 1-time use only).
- The injector has a Needle Guard to protect you after use.

2. Prepare to Use the Acthar Gel single-dose pre-filled SelfJect Injector

- Take the injector out of the refrigerator and remove it from its injector tray to warm at room temperature for a minimum of 45 minutes.

- Do not use the injector right after removing from the refrigerator. The injector does not work as well when cold. Do not heat.
- Check the expiration date (EXP) on the package.
- Complete this injection in a clean, well-lit room.
- Gather alcohol swab, adhesive bandage, and a sharps disposal container.

3. Choose and Clean the Injection Site

- For under the skin (subcutaneous) injection only. - Choose 1 of these sites for injection: - Upper thigh - Belly (abdomen), not within 1-inch of belly button (navel) - Back of arm (only if someone else is giving the injection) - Choose a different site for each injection. - Do not inject through clothing. - Avoid injecting into: - Irritated skin (red, swollen, or painful) - Tattoos, warts, scars, or birthmarks - Within 1-inch of knee or groin area - Stretch marks |  | - Wash your hands well with soap and water.
- For under the skin (subcutaneous) injection only. - Choose 1 of these sites for injection: - Upper thigh - Belly (abdomen), not within 1-inch of belly button (navel) - Back of arm (only if someone else is giving the injection) - Choose a different site for each injection. - Do not inject through clothing. - Avoid injecting into: - Irritated skin (red, swollen, or painful) - Tattoos, warts, scars, or birthmarks - Within 1-inch of knee or groin area - Stretch marks |  | - Clean the injection site with an alcohol swab.

4. Inspect and Uncap

- Inspect the medicine in the Window. The medicine should be a clear light yellow or orange solution.
- Do not use if the medicine is cloudy or you see particles.
- It is normal to see air bubbles.

Pull Bottom Cap off to remove it and throw it away.

- Do not recap the injector as this may damage the needle.
- Avoid touching the Gray Needle Guard.
- Use the injector right away.

5. Inject

(a) Place the injector straight on the cleaned skin at a 90-degree angle. Do not pinch the skin. | (b) Slowly push down the Handle to inject the medicine. Do not lift the injector during the injection. You may hear a "click" when the injection begins. | (c) The injection is complete when the Purple Colored Body disappears and you may hear a "click".

6. Lift and Throw Away (Dispose of)

Lift the injector straight up at a 90-degree angle off the injection site.
The Needle Guard is locked when you see the yellow band.

Place the injector in an approved sharps disposal container according to local regulations.
Do not throw away (dispose of) in your household trash.
SPC-0132 Rev 9

PRINCIPAL DISPLAY PANEL - 5 mL Vial Carton

NDC 63004-8710-1

Acthar®
Gel

(repository corticotropin
injection)

400 USP units/5 mL
(80 USP units/mL)

For intramuscular or
subcutaneous use.

5 mL
multiple-dose vial

Dispense the enclosed
Medication Guide to each
Infantile Spasm patient.

Rx only

PRINCIPAL DISPLAY PANEL - 4 x 0.5 mL Injector Carton

NDC 63004-8712-4
Rx Only

Acthar® Gel
(repository corticotropin injection)

Single-Dose Pre-filled SelfJect™ Injector

40 USP Units/0.5 mL

For Subcutaneous Injection Only
Contains: 4 x 0.5 mL Single-Dose Pre-filled SelfJect™ Injectors
with Quick Reference Guide and 1 x Instructions for Use

PRINCIPAL DISPLAY PANEL - 4 x 1.0 mL Injector Carton

NDC 63004-8711-4
Rx Only

Acthar® Gel
(repository corticotropin injection)

Single-Dose Pre-filled SelfJect™ Injector

80 USP Units/mL

For Subcutaneous Injection Only
Contains: 4 x 1.0 mL Single-Dose Pre-filled SelfJect™ Injectors
with Quick Reference Guide and 1 x Instructions for Use